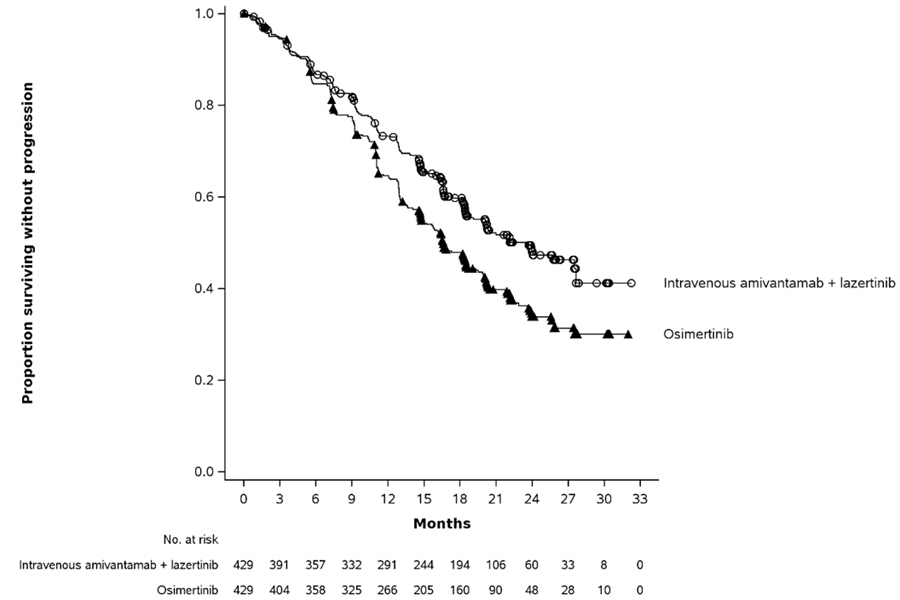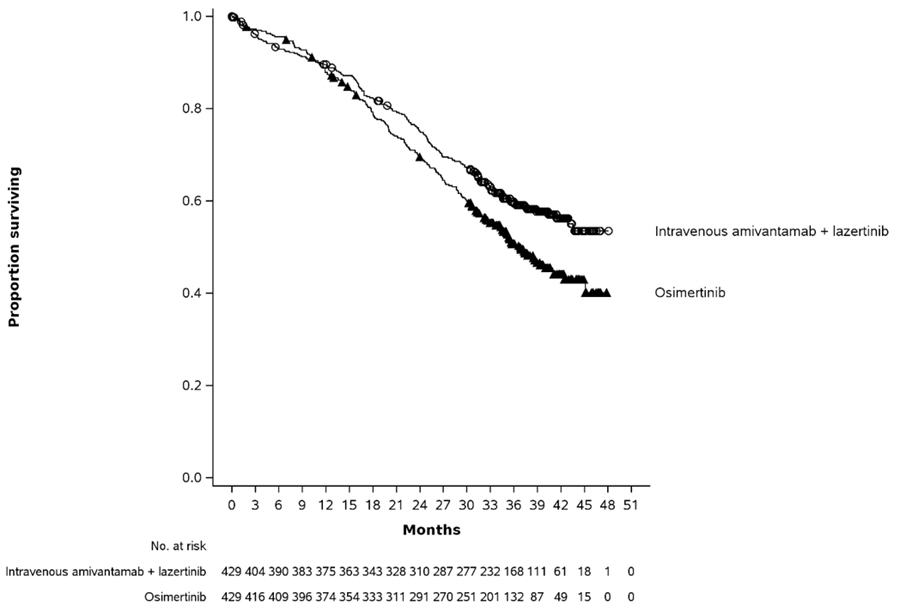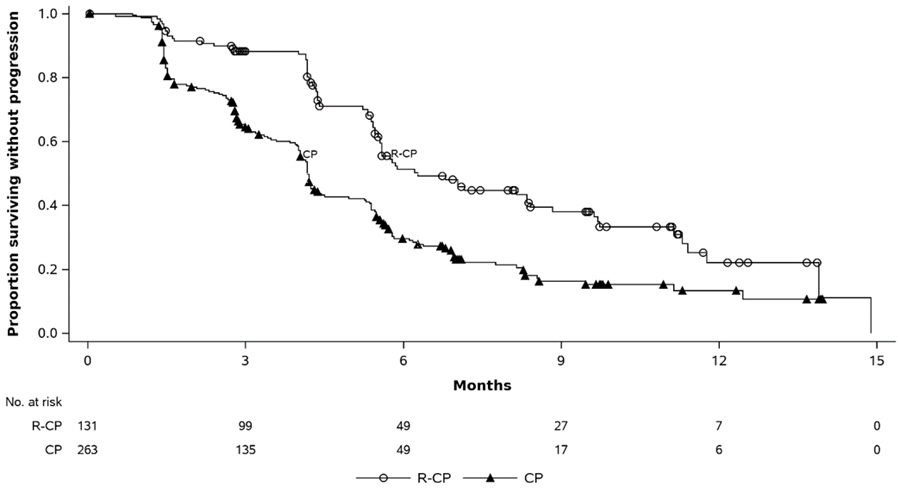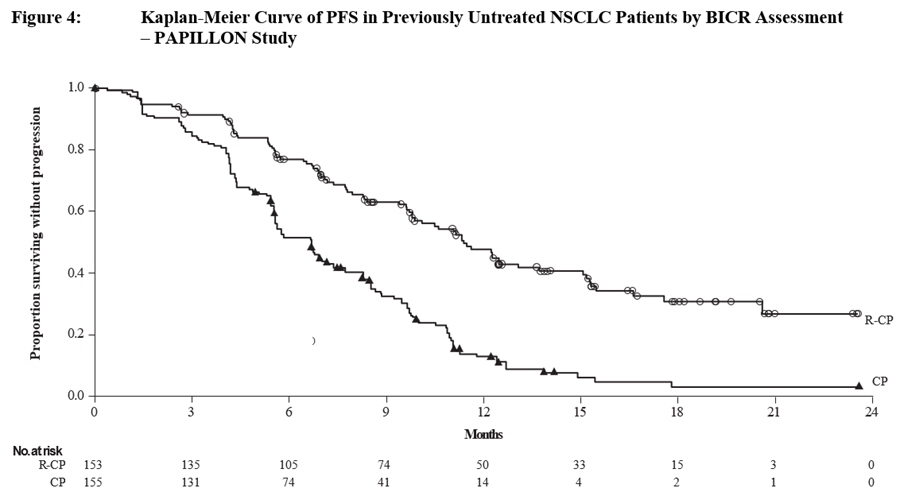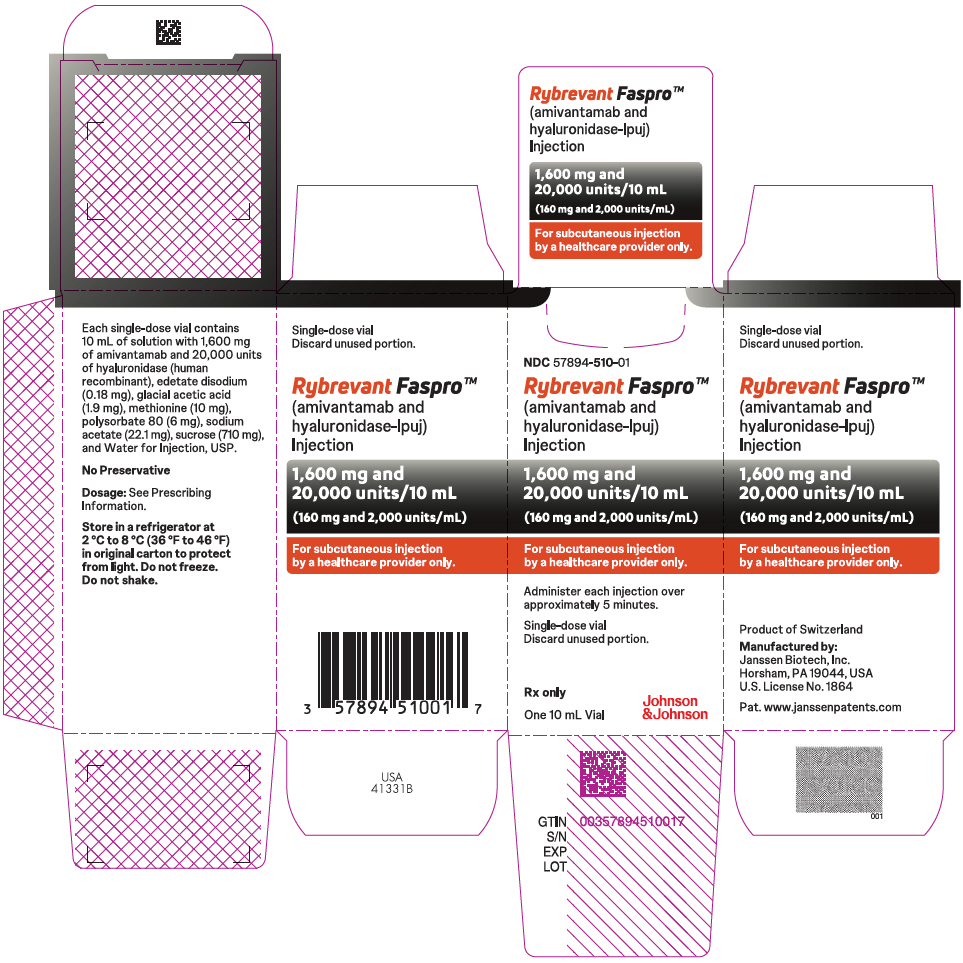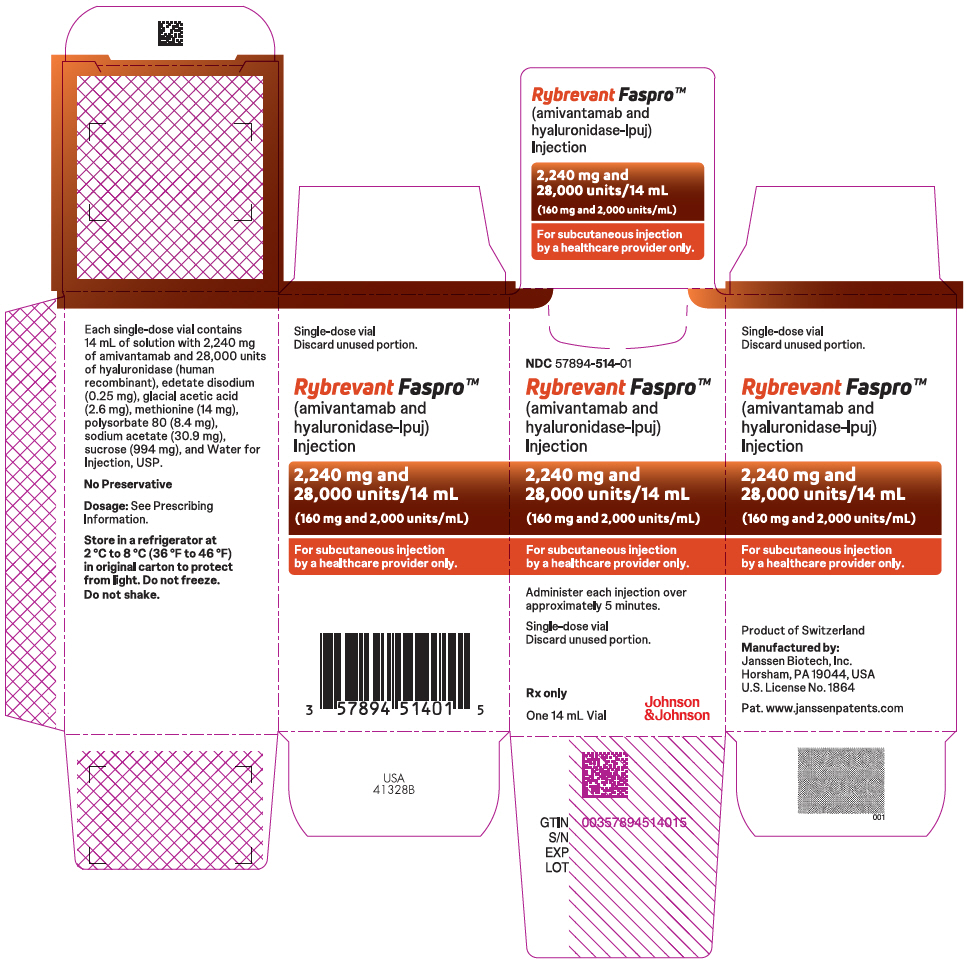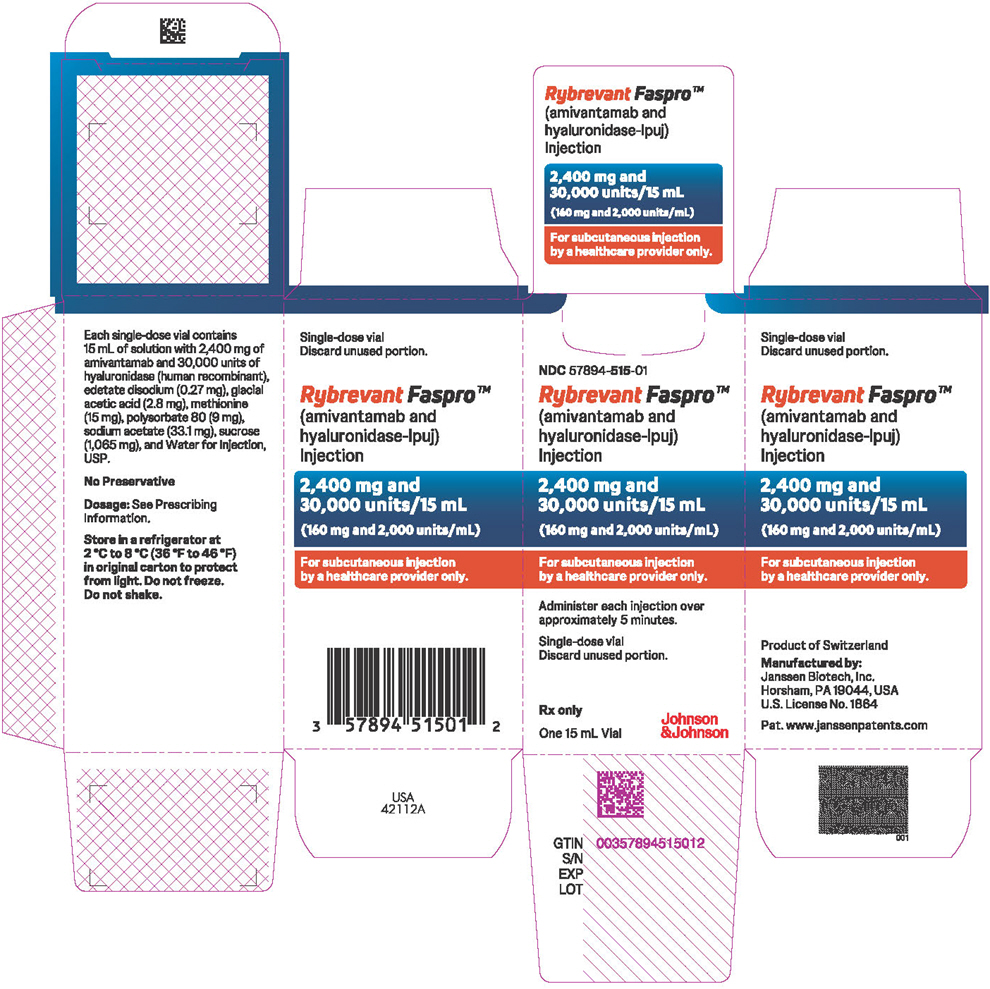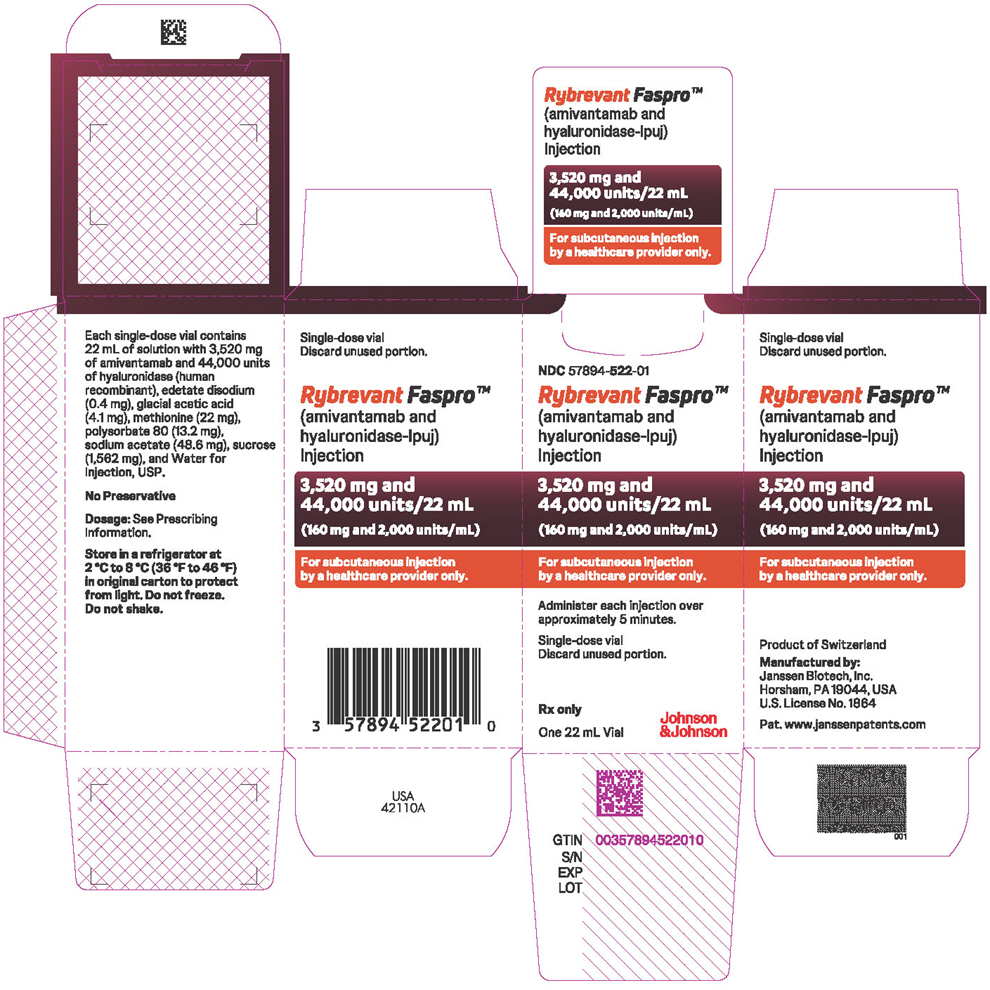 DRUG LABEL: Rybrevant Faspro
NDC: 57894-510 | Form: INJECTION
Manufacturer: Janssen Biotech, Inc.
Category: prescription | Type: HUMAN PRESCRIPTION DRUG LABEL
Date: 20260218

ACTIVE INGREDIENTS: AMIVANTAMAB 1600 mg/10 mL; HYALURONIDASE (HUMAN RECOMBINANT) 20000 mg/10 mL
INACTIVE INGREDIENTS: EDETATE DISODIUM 0.18 mg/10 mL; ACETIC ACID 1.9 mg/10 mL; METHIONINE 10 mg/10 mL; POLYSORBATE 80 6 mg/10 mL; SODIUM ACETATE 22.1 mg/10 mL; SUCROSE 710 mg/10 mL; WATER

HIGHLIGHTS OF PRESCRIBING INFORMATION

These highlights do not include all the information needed to use RYBREVANT FASPRO safely and effectively. See full prescribing information for RYBREVANT FASPRO.
RYBREVANT FASPRO™ (amivantamab and hyaluronidase-lpuj) injection, for subcutaneous use
Initial U.S. Approval: 2025

RECENT MAJOR CHANGES

Dosage and Administration (2.1) | 02/2026
Dosage and Administration (2.3) | 02/2026
Dosage and Administration (2.7) | 02/2026
Dosage and Administration (2.8) | 02/2026
Dosage and Administration (2.9) | 02/2026

1 INDICATIONS AND USAGE

RYBREVANT FASPRO is a combination of amivantamab, a bispecific EGF receptor-directed and MET receptor-directed antibody, and hyaluronidase, an endoglycosidase indicated:

- in combination with lazertinib for the first-line treatment of adult patients with locally advanced or metastatic NSCLC with EGFR exon 19 deletions or exon 21 L858R substitution mutations, as detected by an FDA-approved test. (1, 2.2)
- in combination with carboplatin and pemetrexed for the treatment of adult patients with locally advanced or metastatic NSCLC with EGFR exon 19 deletions or exon 21 L858R substitution mutations, whose disease has progressed on or after treatment with an EGFR tyrosine kinase inhibitor. (1, 2.2)
- in combination with carboplatin and pemetrexed for the first-line treatment of adult patients with locally advanced or metastatic NSCLC with EGFR exon 20 insertion mutations, as detected by an FDA-approved test. (1, 2.2)
- as a single agent for the treatment of adult patients with locally advanced or metastatic NSCLC with EGFR exon 20 insertion mutations, as detected by an FDA-approved test, whose disease has progressed on or after platinum-based chemotherapy. (1, 2.2)

2 DOSAGE AND ADMINISTRATION

For subcutaneous use only. (2.1)

- RYBREVANT FASPRO has different recommended dosage and administration than intravenous amivantamab products. (2.1)
- Administer each injection of RYBREVANT FASPRO subcutaneously in the abdomen over approximately 5 minutes. (2.1)
- The recommended dosage of RYBREVANT FASPRO is based on baseline body weight. (2.3)
- Administer premedications as recommended. (2.4)
- Recommended dosage for RYBREVANT FASPRO in combination with carboplatin and pemetrexed (every 3-week dosing), see Table 2. (2.3)
- Recommended dosage for RYBREVANT FASPRO in combination with lazertinib or for RYBREVANT FASPRO as a single agent (every 4-week dosing), see Table 4. (2.3)
- Recommended dosage for RYBREVANT FASPRO in combination with lazertinib or for RYBREVANT FASPRO as a single agent (every 2-week dosing), see Table 5. (2.3)

3 DOSAGE FORMS AND STRENGTHS

Injection: 1,600 mg amivantamab and 20,000 units hyaluronidase per 10 mL (160 mg and 2,000 units/mL) solution in a single-dose vial. (3)

2,240 mg amivantamab and 28,000 units hyaluronidase per 14 mL (160 mg and 2,000 units/mL) solution in a single-dose vial. (3)

2,400 mg amivantamab and 30,000 units hyaluronidase per 15 mL (160 mg and 2,000 units/mL) solution in a single-dose vial. (3)

3,520 mg amivantamab and 44,000 units hyaluronidase per 22 mL (160 mg and 2,000 units/mL) solution in a single-dose vial. (3)

4 CONTRAINDICATIONS

Patients with known hypersensitivity to hyaluronidase or to any of its excipients. (4)

5 WARNINGS AND PRECAUTIONS

- Hypersensitivity and Administration-Related Reactions (ARR): Premedicate with antihistamines, antipyretics, and glucocorticoids. Monitor patients for any signs and symptoms of ARRs. Resume treatment upon resolution of symptoms or permanently discontinue RYBREVANT FASPRO based on severity. (2.8, 5.1)
- Interstitial Lung Disease (ILD)/Pneumonitis: Monitor for new or worsening symptoms indicative of ILD/pneumonitis. Immediately withhold RYBREVANT FASPRO in patients with suspected ILD/pneumonitis and permanently discontinue if ILD/pneumonitis is confirmed. (2.8, 5.2)
- Venous Thromboembolic (VTE) Events with Concomitant Use with Lazertinib: Prophylactic anticoagulation is recommended for the first four months of treatment. Monitor for signs and symptoms of VTE and treat as medically appropriate. Withhold RYBREVANT FASPRO and lazertinib based on severity. Once anticoagulant treatment has been initiated, resume RYBREVANT FASPRO and lazertinib at the same dose at the discretion of the healthcare provider. Permanently discontinue RYBREVANT FASPRO and continue lazertinib for recurrent VTE despite therapeutic anticoagulation. (2.8, 5.3)
- Dermatologic Adverse Reactions: Can cause severe rash including toxic epidermal necrolysis (TEN) and dermatitis acneiform. At treatment initiation, prophylactic and concomitant medications are recommended. Withhold, dose reduce or permanently discontinue RYBREVANT FASPRO based on severity. (2.5, 2.8, 5.4)
- Ocular Toxicity: Promptly refer patients with new or worsening eye symptoms to an ophthalmologist. Withhold, dose reduce or permanently discontinue RYBREVANT FASPRO based on severity. (5.5)
- Embryo-Fetal Toxicity: Can cause fetal harm. Advise females of reproductive potential of the potential risk to the fetus and to use effective contraception. (5.6, 8.1, 8.3)

6 ADVERSE REACTIONS

RYBREVANT FASPRO in Combination with Lazertinib

- The most common adverse reactions (≥ 20%) were rash, nail toxicity, musculoskeletal pain, fatigue, stomatitis, edema, nausea, diarrhea, vomiting, constipation, decreased appetite, and headache. (6.1)
- The most common Grade 3 or 4 laboratory abnormalities (≥ 2%) were decreased lymphocyte count, decreased sodium, decreased potassium, decreased albumin, increased alanine aminotransferase, increased aspartate aminotransferase, decreased platelet count, increased gamma-glutamyl transferase, and decreased hemoglobin. (6.1)

Intravenous Amivantamab in Combination with Lazertinib

- The most common adverse reactions (≥ 20%) were rash, nail toxicity, infusion-related reaction, musculoskeletal pain, stomatitis, edema, VTE, paresthesia, fatigue, diarrhea, constipation, COVID-19, hemorrhage, dry skin, decreased appetite, pruritus, and nausea. (6.1)
- The most common Grade 3 or 4 laboratory abnormalities (≥ 2%) were decreased albumin, decreased sodium, increased ALT, decreased potassium, decreased hemoglobin, increased AST, increased GGT, and increased magnesium. (6.1)

Intravenous Amivantamab in Combination with Carboplatin and Pemetrexed

- The most common adverse reactions (≥ 20%) were rash, nail toxicity, infusion-related reaction, fatigue, nausea, stomatitis, constipation, edema, decreased appetite, musculoskeletal pain, vomiting, and COVID-19. (6.1)
- The most common Grade 3 or 4 laboratory abnormalities (≥ 2%) were decreased neutrophils, decreased leukocytes, decreased platelets, decreased hemoglobin, decreased potassium, decreased sodium, increased alanine aminotransferase, increased gamma-glutamyl transferase, and decreased albumin. (6.1)

Intravenous Amivantamab as a Single Agent

- The most common adverse reactions (≥ 20%) were rash, infusion-related reaction, paronychia, musculoskeletal pain, dyspnea, nausea, edema, cough, fatigue, stomatitis, constipation, vomiting, and pruritus. (6.1)
- The most common Grade 3 or 4 laboratory abnormalities (≥ 2%) were increased gamma-glutamyl transferase, decreased sodium, decreased potassium, and increased alkaline phosphatase. (6.1)

To report SUSPECTED ADVERSE REACTIONS, contact Janssen Biotech, Inc. at 1-800-526-7736 or FDA at 1-800-FDA-1088 or www.fda.gov/medwatch.

8 USE IN SPECIFIC POPULATIONS

Lactation: Advise not to breastfeed. (8.2)

FULL PRESCRIBING INFORMATION

1 INDICATIONS AND USAGE

1.1 First-Line Treatment of NSCLC with EGFR Exon 19 Deletions or Exon 21 L858R Substitution Mutations

RYBREVANT FASPRO, in combination with lazertinib, is indicated for the first-line treatment of adult patients with locally advanced or metastatic non-small cell lung cancer (NSCLC) with epidermal growth factor receptor (EGFR) exon 19 deletions or exon 21 L858R substitution mutations, as detected by an FDA-approved test [see Dosage and Administration (2.2)].

1.2 Previously Treated NSCLC with EGFR Exon 19 Deletions or Exon 21 L858R Substitution Mutations

RYBREVANT FASPRO, in combination with carboplatin and pemetrexed, is indicated for the treatment of adult patients with locally advanced or metastatic NSCLC with EGFR exon 19 deletions or exon 21 L858R substitution mutations, whose disease has progressed on or after treatment with an EGFR tyrosine kinase inhibitor [see Dosage and Administration (2.2)].

1.3 First-Line Treatment of NSCLC with EGFR Exon 20 Insertion Mutations

RYBREVANT FASPRO, in combination with carboplatin and pemetrexed, is indicated for the first-line treatment of adult patients with locally advanced or metastatic NSCLC with EGFR exon 20 insertion mutations, as detected by an FDA-approved test [see Dosage and Administration (2.2)].

1.4 Previously Treated NSCLC with EGFR Exon 20 Insertion Mutations

RYBREVANT FASPRO is indicated as a single agent for the treatment of adult patients with locally advanced or metastatic NSCLC with EGFR exon 20 insertion mutations, as detected by an FDA-approved test [see Dosage and Administration (2.2)], whose disease has progressed on or after platinum-based chemotherapy.

2 DOSAGE AND ADMINISTRATION

2.1 Important Dosage and Administration Information

- RYBREVANT FASPRO is for subcutaneous use only. Do not administer RYBREVANT FASPRO intravenously.
- RYBREVANT FASPRO must be administered by a healthcare professional.
- To reduce the risk of medication errors, prior to administration, check the vial labels to ensure that the drug being prepared and administered is subcutaneous RYBREVANT FASPRO and not intravenous amivantamab.
- RYBREVANT FASPRO has different recommended dosage and administration than intravenous amivantamab products. Do not substitute RYBREVANT FASPRO for or with intravenous amivantamab products.
- Adult patients currently receiving intravenous amivantamab at an every 2-week dosing regimen may switch to subcutaneous RYBREVANT FASPRO at an every 2-week dosing regimen or at an every 4-week dosing regimen at their next scheduled dose on or after Week 5.
- Adult patients currently receiving intravenous amivantamab at an every 3-week dosing regimen may switch to subcutaneous RYBREVANT FASPRO at an every 3-week dosing regimen at their next scheduled dose on or after Week 4.
- Adult patients currently receiving RYBREVANT FASPRO at an every 2-week dosing regimen may switch to an every 4-week dosing regimen at their next scheduled dose on or after Week 5.
- RYBREVANT FASPRO is not indicated for use in pediatric patients.
- Administer premedications before each RYBREVANT FASPRO dose as recommended, to reduce the risk of administration-related reactions (ARRs) [see Dosage and Administration (2.4)].
- Administer each injection of RYBREVANT FASPRO subcutaneously in the abdomen over approximately 5 minutes to minimize injection site irritation. Do not inject into tattoos or scars or areas where the skin is red, bruised, tender, hard, not intact or within 2 inches (5 cm) around the periumbilical area.
- If the total dose requires multiple injections of RYBREVANT FASPRO, administer each injection consecutively in separate quadrants of the abdomen, with each injection taking approximately 5 minutes.
- Rotate injection sites at the next scheduled dose.
- Pause or slow the delivery rate if the patient experiences pain. In the event pain is not alleviated by pausing or slowing down delivery rate, a second injection site may be chosen on the opposite side of the abdomen to deliver the remainder of the dose.
- If administering with a subcutaneous infusion set, ensure that the full dose is delivered through the infusion set, 0.9% sodium chloride solution may be utilized to flush remaining drug product through the line.
- Discard unused portion.

2.2 Patient Selection

Select patients for treatment with RYBREVANT FASPRO based on the presence of a mutation as detected by an FDA-approved test as shown in Table 1.

Table 1: Patient Selection
Indication | Treatment Regimen | Source for Testing
First-Line Treatment of NSCLC with EGFR Exon 19 Deletions or Exon 21 L858R Substitution Mutations [see Indications and Usage (1.1)] | RYBREVANT FASPRO in combination with lazertinib | - Tumor or plasma specimens. - Testing may be performed at any time from initial diagnosis. - Testing does not need to be repeated once EGFR mutation status has been established.
Previously treated locally advanced or metastatic NSCLC with EGFR Exon 19 deletions or Exon 21 L858R substitution mutations (progressive disease on an EGFR tyrosine kinase inhibitor) [see Indications and Usage (1.2)] | RYBREVANT FASPRO in combination with carboplatin and pemetrexed | - Tumor or plasma specimens. - Testing may be performed at any time from initial diagnosis. - Testing does not need to be repeated once EGFR mutation status has been established.
First-Line Treatment of NSCLC with EGFR Exon 20 Insertion Mutations [see Indications and Usage (1.3)] | RYBREVANT FASPRO in combination with carboplatin and pemetrexed | - Tumor or plasma specimens. - Testing may be performed at any time from initial diagnosis. - Testing does not need to be repeated once EGFR mutation status has been established.
Previously Treated NSCLC with EGFR Exon 20 Insertion Mutations [see Indications and Usage (1.4)] | RYBREVANT FASPRO as a single agent | - Tumor or plasma specimens. - Testing may be performed at any time from initial diagnosis. - Testing does not need to be repeated once EGFR mutation status has been established.
Information on FDA-approved tests is available at: http://www.fda.gov/CompanionDiagnostics.

2.3 Recommended Dosage

RYBREVANT FASPRO In Combination with Carboplatin and Pemetrexed - Every 3-Week Dosing

The recommended dosages of RYBREVANT FASPRO, administered every 3 weeks in combination with carboplatin and pemetrexed, based on baseline body weight are provided in Table 2. Administer RYBREVANT FASPRO until disease progression or unacceptable toxicity.

Table 2: Recommended Dosage for RYBREVANT FASPRO in Combination with Carboplatin and Pemetrexed (Every 3-Week Dosing)
Body Weight at Baseline [Dose adjustments not required for subsequent body weight changes.] | Recommended Dose | Dosing Schedule
Less than 80 kg | 1,600 mg amivantamab and 20,000 units hyaluronidase | First dose at Week 1 Day 1
Less than 80 kg | 2,400 mg amivantamab and 30,000 units hyaluronidase | Weekly (total of 2 doses) from Weeks 2 to 3; - Weeks 2 to 3 – Injection on Day 1
Less than 80 kg | 2,400 mg amivantamab and 30,000 units hyaluronidase | Every 3 weeks starting at Week 4 onwards
Greater than or equal to 80 kg | 2,240 mg amivantamab and 28,000 units hyaluronidase | First dose at Week 1 Day 1
Greater than or equal to 80 kg | 3,360 mg amivantamab and 42,000 units hyaluronidase | Weekly (total of 2 doses) from Weeks 2 to 3; - Weeks 2 to 3 – Injection on Day 1
Greater than or equal to 80 kg | 3,360 mg amivantamab and 42,000 units hyaluronidase | Every 3 weeks starting at Week 4 onwards

The recommended order of administration and regimen for RYBREVANT FASPRO in combination with carboplatin and pemetrexed are provided in Table 3.

Table 3: Order of Administration and Regimen for RYBREVANT FASPRO in Combination with Carboplatin and Pemetrexed
Administer the regimen in the following order: pemetrexed first, carboplatin second, and RYBREVANT FASPRO last.
Drug | Dose | Duration/Timing of Treatment
Pemetrexed | Pemetrexed 500 mg/m^2 intravenously Refer to the pemetrexed Full Prescribing Information for complete information. | Every 3 weeks, continue until disease progression or unacceptable toxicity.
Carboplatin | Carboplatin AUC 5 intravenously Refer to the carboplatin Full Prescribing Information for complete information. | Every 3 weeks for up to 12 weeks.
RYBREVANT FASPRO | RYBREVANT FASPRO subcutaneously. See Table 2. | Every 3 weeks, continue until disease progression or unacceptable toxicity.

RYBREVANT FASPRO in Combination with Lazertinib or as a Single Agent – Every 4-Week or Every 2-Week Dosing

The recommended dosages of RYBREVANT FASPRO in combination with lazertinib or as a single agent, based on baseline body weight, are provided in Table 4 (every 4-week dosing) and Table 5 (every 2-week dosing).

Administer RYBREVANT FASPRO until disease progression or unacceptable toxicity.

Table 4: Recommended Dosage for RYBREVANT FASPRO in Combination with Lazertinib or for RYBREVANT FASPRO as a Single Agent (Every 4-Week Dosing)
Body Weight at Baseline [Dose adjustments not required for subsequent body weight changes.] | Recommended Dose | Dosing Schedule
Less than 80 kg | 1,600 mg amivantamab and 20,000 units hyaluronidase | Weekly (total of 4 doses) from Weeks 1 to 4; - Weeks 1 to 4 – Injection on Day 1
Less than 80 kg | 3,520 mg amivantamab and 44,000 units hyaluronidase | Every 4 weeks starting at Week 5 onwards
Greater than or equal to 80 kg | 2,240 mg amivantamab and 28,000 units hyaluronidase | Weekly (total of 4 doses) from Weeks 1 to 4; - Weeks 1 to 4 – Injection on Day 1
Greater than or equal to 80 kg | 4,640 mg amivantamab and 58,000 units hyaluronidase | Every 4 weeks starting at Week 5 onwards

Table 5: Recommended Dosage for RYBREVANT FASPRO in Combination with Lazertinib or for RYBREVANT FASPRO as a Single Agent (Every 2-Week Dosing)
Body Weight at Baseline [Dose adjustments not required for subsequent body weight changes.] | Recommended Dose | Dosing Schedule
Less than 80 kg | 1,600 mg amivantamab and 20,000 units hyaluronidase | Weekly (total of 4 doses) from Weeks 1 to 4; - Weeks 1 to 4 – Injection on Day 1
Less than 80 kg | 1,600 mg amivantamab and 20,000 units hyaluronidase | Every 2 weeks starting at Week 5 onwards [May switch to RYBREVANT FASPRO every 4-week dosing regimen at their next scheduled dose on or after Week 5. See Table 4 for every 4-week dosing information.]
Greater than or equal to 80 kg | 2,240 mg amivantamab and 28,000 units hyaluronidase | Weekly (total of 4 doses) from Weeks 1 to 4; - Weeks 1 to 4 – Injection on Day 1
Greater than or equal to 80 kg | 2,240 mg amivantamab and 28,000 units hyaluronidase | Every 2 weeks starting at Week 5 onwards

RYBREVANT FASPRO in Combination with Lazertinib

Order of Administration

When given in combination with lazertinib, administer RYBREVANT FASPRO any time after lazertinib when given on the same day. Refer to the lazertinib prescribing information for recommended lazertinib dosing information. Administer RYBREVANT FASPRO in combination with lazertinib until disease progression or unacceptable toxicity.

2.4 Recommended Premedications

Prior to the initial injection of RYBREVANT FASPRO (Week 1 Day 1), administer premedications as described in Table 6 to reduce the risk of administration-related reactions [see Warnings and Precautions (5.1)].

Glucocorticoid administration is required at the initial dose at Week 1 Day 1 only, and upon re-initiation after prolonged dose interruptions, then as necessary for subsequent injections. Administer both antihistamine and antipyretic prior to all RYBREVANT FASPRO doses.

Table 6: Premedications
Medication | Dose | Route of Administration | Dosing Window Prior to RYBREVANT FASPRO Administration
Antihistamine [Required at all doses.] | Diphenhydramine (25 mg to 50 mg) or equivalent | Intravenous | 15 to 30 minutes
Antihistamine [Required at all doses.] | Diphenhydramine (25 mg to 50 mg) or equivalent | Oral | 30 to 60 minutes
Antipyretic | Acetaminophen (650 mg to 1,000 mg) or equivalent | Intravenous | 15 to 30 minutes
Antipyretic | Acetaminophen (650 mg to 1,000 mg) or equivalent | Oral | 30 to 60 minutes
Glucocorticoid [Required at initial dose (Week 1, Day 1) or at the next subsequent dose in the event of an administration-related reaction.] | Dexamethasone (20 mg) or equivalent | Intravenous | 45 to 60 minutes
Glucocorticoid [Required at initial dose (Week 1, Day 1) or at the next subsequent dose in the event of an administration-related reaction.] | Dexamethasone (20 mg) or equivalent | Oral | At least 60 minutes
Glucocorticoid [Optional for subsequent doses.] | Dexamethasone (10 mg) or equivalent | Intravenous | 45 to 60 minutes
Glucocorticoid [Optional for subsequent doses.] | Dexamethasone (10 mg) or equivalent | Oral | 60 to 90 minutes

2.5 Prophylactic and Concomitant Medications to Reduce the Risk of Dermatologic Adverse Reactions

When initiating treatment with RYBREVANT FASPRO, prophylactic and concomitant medications are recommended to reduce the risk and severity of dermatologic adverse reactions [see Warnings and Precautions (5.4)].

- Administer an oral antibiotic (doxycycline or minocycline, 100 mg orally twice daily) starting on Day 1 for the first 12 weeks of treatment.
- After completion of oral antibiotic treatment, administer antibiotic lotion to the scalp (clindamycin 1% topical once daily) for the next 9 months of treatment.
- Administer non-comedogenic skin moisturizer (ceramide-based or other formulations that provide long-lasting skin hydration and exclude drying agents) on the face and whole body (except scalp).
- Wash hands and feet with 4% chlorhexidine solution once daily.
- Limit sun exposure during and for 2 months after treatment. Advise patients to wear protective clothing and use broad-spectrum UVA/UVB sunscreen to reduce the risk of dermatologic adverse reactions.

2.6 RYBREVANT FASPRO in Combination with Lazertinib: Concomitant Medications to Reduce the Risk of Venous Thromboembolic Events

When initiating treatment with RYBREVANT FASPRO in combination with lazertinib, administer anticoagulant prophylaxis to prevent venous thromboembolic (VTE) events for the first four months of treatment [see Warnings and Precautions (5.3)]. If there are no signs or symptoms of VTE during the first four months of treatment, consider discontinuation of anticoagulant prophylaxis at the discretion of the healthcare provider. Refer to the lazertinib prescribing information for information about concomitant medications.

2.7 Missed Dose

For a 4-week or 2-week dosing schedule:

- If a dose of RYBREVANT FASPRO is missed between Weeks 1 to 4, administer within 24 hours.
- If a dose of RYBREVANT FASPRO is missed from Week 5 onward, administer within 7 days.

For a 3-week dosing schedule:

- If a dose of RYBREVANT FASPRO is missed between Weeks 1 to 3, administer within 24 hours.
- If a dose of RYBREVANT FASPRO is missed from Week 4 onward, administer within 7 days.

If the missed dose is not administered according to this guidance, do not administer the missed dose and administer the next dose per the usual dosing schedule.

2.8 Dosage Modifications for Adverse Reactions

The recommended dose reductions for adverse reactions for RYBREVANT FASPRO are listed in Table 7.

Table 7: Dose Reductions for Adverse Reactions for RYBREVANT FASPRO
Dose at which the adverse reaction occurred | 1st Dose Reduction | 2nd Dose Reduction | 3rd Dose Reduction
1,600 mg amivantamab and 20,000 units hyaluronidase | 1,050 mg amivantamab and 13,200 units hyaluronidase [The dose volume should be 6.6 mL for 1,050 mg amivantamab and 13,200 units hyaluronidase dose.] | 700 mg amivantamab and 8,800 units hyaluronidase [The dose volume should be 4.4 mL for 700 mg amivantamab and 8,800 units hyaluronidase dose.] | Discontinue RYBREVANT FASPRO
2,240 mg amivantamab and 28,000 units hyaluronidase | 1,600 mg amivantamab and 20,000 units hyaluronidase [The dose volume should be 10 mL for 1,600 mg amivantamab and 20,000 units hyaluronidase dose.] | 1,050 mg amivantamab and 13,200 units hyaluronidase | Discontinue RYBREVANT FASPRO
2,400 mg amivantamab and 30,000 units hyaluronidase | 1,600 mg amivantamab and 20,000 units hyaluronidase | 1,050 mg amivantamab and 13,200 units hyaluronidase | Discontinue RYBREVANT FASPRO
3,360 mg amivantamab and 42,000 units hyaluronidase | 2,240 mg amivantamab and 28,000 units hyaluronidase [The dose volume should be 14 mL for 2,240 mg amivantamab and 28,000 units hyaluronidase dose.] | 1,600 mg amivantamab and 20,000 units hyaluronidase | Discontinue RYBREVANT FASPRO
3,520 mg amivantamab and 44,000 units hyaluronidase | 2,400 mg amivantamab and 30,000 units hyaluronidase [The dose volume should be 15 mL for 2,400 mg amivantamab and 30,000 units hyaluronidase dose.] | 1,600 mg amivantamab and 20,000 units hyaluronidase | Discontinue RYBREVANT FASPRO
4,640 mg amivantamab and 58,000 units hyaluronidase | 3,360 mg amivantamab and 42,000 units hyaluronidase [The dose volume should be 21 mL for 3,360 mg amivantamab and 42,000 units hyaluronidase dose.] | 2,240 mg amivantamab and 28,000 units hyaluronidase | Discontinue RYBREVANT FASPRO

The recommended dosage modifications and management for adverse reactions for RYBREVANT FASPRO are provided in Table 8.

Table 8: Recommended Dosage Modifications and Management for Adverse Reactions for RYBREVANT FASPRO
Adverse Reaction | Severity | Dosage Modifications
Hypersensitivity and Administration-Related Reactions (ARRs) [see Warnings and Precautions (5.1)] | Grade 1 or 2 | - Interrupt RYBREVANT FASPRO injection if ARR is suspected and monitor patient until reaction symptoms resolve. - Resume injection upon resolution of symptoms. - Include corticosteroid with premedications for subsequent dose (see Table 6).
Hypersensitivity and Administration-Related Reactions (ARRs) [see Warnings and Precautions (5.1)] | Grade 3 | - Interrupt RYBREVANT FASPRO injection and administer supportive care medications. Continuously monitor patient until reaction symptoms resolve. - Resume injection upon resolution of symptoms. - Include corticosteroid with premedications for subsequent dose (see Table 6). For recurrent Grade 3, permanently discontinue RYBREVANT FASPRO.
Hypersensitivity and Administration-Related Reactions (ARRs) [see Warnings and Precautions (5.1)] | Grade 4 | Permanently discontinue RYBREVANT FASPRO.
Interstitial Lung Disease (ILD)/pneumonitis [see Warnings and Precautions (5.2)] | Any Grade | - Withhold RYBREVANT FASPRO if ILD/pneumonitis is suspected. - Permanently discontinue RYBREVANT FASPRO if ILD/pneumonitis is confirmed.
Venous Thromboembolic (VTE) Events [Applies to the combination with lazertinib, see Warnings and Precautions (5.3)] | Grade 2 or 3 | - Withhold RYBREVANT FASPRO and lazertinib. - Administer anticoagulation treatment as clinically indicated. - Once anticoagulant treatment has been initiated, resume RYBREVANT FASPRO and lazertinib at the same dose level, at the discretion of the treating physician.
Venous Thromboembolic (VTE) Events [Applies to the combination with lazertinib, see Warnings and Precautions (5.3)] | Grade 4 or recurrent Grade 2 or 3 despite therapeutic level anticoagulation | - Withhold lazertinib and permanently discontinue RYBREVANT FASPRO. - Administer anticoagulation treatment as clinically indicated. - Once anticoagulant treatment has been initiated, treatment can continue with lazertinib at the same dose level at the discretion of the treating physician.
Dermatologic Adverse Reactions (including dermatitis acneiform, pruritus, dry skin) [see Warnings and Precautions (5.4)] | Grade 1 or 2 | - Initiate supportive care management as clinically indicated. - Reassess after 2 weeks; if rash does not improve, consider dose reduction.
Dermatologic Adverse Reactions (including dermatitis acneiform, pruritus, dry skin) [see Warnings and Precautions (5.4)] | Grade 3 | - Withhold RYBREVANT FASPRO and initiate supportive care management as clinically indicated. - Upon recovery to Grade ≤ 2, resume RYBREVANT FASPRO at reduced dose. - If no improvement within 2 weeks, permanently discontinue treatment.
Dermatologic Adverse Reactions (including dermatitis acneiform, pruritus, dry skin) [see Warnings and Precautions (5.4)] | Grade 4 or Severe bullous, blistering or exfoliating skin conditions (including toxic epidermal necrolysis (TEN) | Permanently discontinue RYBREVANT FASPRO.
Other Adverse Reactions [see Adverse Reactions (6.1)] | Grade 3 | - Withhold RYBREVANT FASPRO until recovery to Grade ≤ 1 or baseline. - Resume at the same dose if recovery occurs within 1 week. - Resume at reduced dose if recovery occurs after 1 week but within 4 weeks. - Permanently discontinue if recovery does not occur within 4 weeks.
Other Adverse Reactions [see Adverse Reactions (6.1)] | Grade 4 | - Withhold RYBREVANT FASPRO until recovery to Grade ≤ 1 or baseline. - Resume at reduced dose if recovery occurs within 4 weeks. - Permanently discontinue if recovery does not occur within 4 weeks. - Permanently discontinue for recurrent Grade 4 reactions.

Recommended Dosage Modifications for Adverse Reactions for RYBREVANT FASPRO in Combination with Lazertinib

When administering RYBREVANT FASPRO in combination with lazertinib, if there is an adverse reaction requiring dose reduction after withholding treatment and resolution, reduce the dose of RYBREVANT FASPRO first. Refer to the lazertinib prescribing information for information about dosage modifications for lazertinib.

Recommended Dosage Modifications for Adverse Reactions for RYBREVANT FASPRO in Combination with Carboplatin and Pemetrexed

When administering RYBREVANT FASPRO in combination with carboplatin and pemetrexed, modify the dosage of one or more drugs. Withhold or discontinue RYBREVANT FASPRO as shown in Table 8. Refer to prescribing information for carboplatin and pemetrexed for additional dosage modification information.

2.9 Preparation Instructions

- For important information on RYBREVANT FASPRO dosage and administration, see Dosage and Administration (2.1).
- Do not dilute RYBREVANT FASPRO.
- RYBREVANT FASPRO does not contain an antimicrobial preservative. Administer RYBREVANT FASPRO dose in prepared syringes immediately. If the RYBREVANT FASPRO dose is not administered immediately, refer to "Storage" [see Dosage and Administration (2.9)].
- RYBREVANT FASPRO is a clear to opalescent and colorless to pale yellow solution. Parenteral drug products should be inspected visually for particulate matter and discoloration prior to administration, whenever solution and container permit. Do not use if the solution is discolored, or cloudy, or if foreign particles are present.
- Remove the appropriate number of RYBREVANT FASPRO vial(s) from refrigeration and equilibrate RYBREVANT FASPRO to room temperature [15 °C to 30 °C (59 °F to 86 °F)] for at least 15 minutes. Do not warm RYBREVANT FASPRO in any other way. Do not shake.
- Withdraw the required injection volume of RYBREVANT FASPRO (see Table 9) from the vial(s) into a syringe(s) using a transfer needle. Discard unused portion.
- RYBREVANT FASPRO is compatible with stainless steel injection needles, polypropylene and polycarbonate syringes, and polyethylene, polyurethane, and polyvinylchloride subcutaneous infusion sets. Use 0.9% Sodium Chloride Injection to flush an infusion set, if needed.
- Administer using a 21G to 23G needle or infusion set to ensure ease of administration. If immediate administration is not possible, replace the transfer needle with a syringe closing cap for transport.
- Divide doses requiring greater than 15 mL into approximately equal volumes in two syringes and administer at separate injection sites. Do NOT exceed 15 mL in each syringe.

The dose volumes are provided in Table 9.

Table 9: Dosing Volumes for RYBREVANT FASPRO
RYBREVANT FASPRO Total Dose | Total Dose Volume
1,600 mg amivantamab and 20,000 units hyaluronidase | 10 mL
2,240 mg amivantamab and 28,000 units hyaluronidase | 14 mL
2,400 mg amivantamab and 30,000 units hyaluronidase | 15 mL
3,360 mg amivantamab and 42,000 units hyaluronidase | 21 mL [For the 21 mL dose volume, the entire contents of the 3,520 mg amivantamab and 44,000 units hyaluronidase/22 mL vial will not be needed. Discard unused portion.] [Divide the dose volume approximately equally into two syringes (each syringe should not exceed 15 mL).]
3,520 mg amivantamab and 44,000 units hyaluronidase | 22 mL
4,640 mg amivantamab and 58,000 units hyaluronidase | 29 mL [For the 29 mL dose volume, use one 2,240 mg amivantamab and 28,000 units hyaluronidase/14 mL vial and one 2,400 mg amivantamab and 30,000 units hyaluronidase/15 mL vial to minimize waste. If a different combination of vials is used, discard unused portion.]

Storage

- If immediate administration is not possible, store the prepared syringes of RYBREVANT FASPRO refrigerated at 2 °C to 8 °C (36 °F to 46 °F) for up to 24 hours followed by at room temperature of 15 °C to 30 °C (59 °F to 86 °F) for up to 24 hours.
- Discard the prepared syringe(s) if stored for more than 24 hours refrigerated or more than 24 hours at room temperature. If stored in the refrigerator, allow the solution to come to room temperature before administration.

3 DOSAGE FORMS AND STRENGTHS

Injection

- 1,600 mg amivantamab and 20,000 units hyaluronidase per 10 mL (160 mg and 2,000 units/mL) clear to opalescent and colorless to pale yellow solution in a single-dose vial.
- 2,240 mg amivantamab and 28,000 units hyaluronidase per 14 mL (160 mg and 2,000 units/mL) clear to opalescent and colorless to pale yellow solution in a single-dose vial.
- 2,400 mg amivantamab and 30,000 units hyaluronidase per 15 mL (160 mg and 2,000 units/mL) clear to opalescent and colorless to pale yellow solution in a single-dose vial.
- 3,520 mg amivantamab and 44,000 units hyaluronidase per 22 mL (160 mg and 2,000 units/mL) clear to opalescent and colorless to pale yellow solution in a single-dose vial.

4 CONTRAINDICATIONS

RYBREVANT FASPRO is contraindicated in patients with known hypersensitivity to hyaluronidase or to any of its excipients.

5 WARNINGS AND PRECAUTIONS

5.1 Hypersensitivity and Administration-Related Reactions

RYBREVANT FASPRO can cause hypersensitivity and administration-related reactions (ARR); signs and symptoms of ARR include dyspnea, flushing, fever, chills, chest discomfort, hypotension, and vomiting. The median time to ARR onset is approximately 2 hours. Local injection site reactions are described separately in Section 6.1.

RYBREVANT FASPRO (Subcutaneous Amivantamab) with Lazertinib

In PALOMA-3 [see Adverse Reactions (6.1)], in the 206 patients who received RYBREVANT FASPRO in combination with lazertinib, all Grade ARR occurred in 13%, including 0.5% Grade 3. Of the patients who experienced ARR, 89% occurred with the initial dose (Week 1, Day 1).

Premedicate with antihistamines, antipyretics, and glucocorticoids and administer RYBREVANT FASPRO as recommended [see Dosage and Administration (2.4)].

Monitor patients for any signs and symptoms of administration-related reactions during injection in a setting where cardiopulmonary resuscitation medication and equipment are available. Interrupt RYBREVANT FASPRO injection, if ARR is suspected. Resume treatment upon resolution of symptoms or permanently discontinue RYBREVANT FASPRO based on severity [see Dosage and Administration (2.8)].

5.2 Interstitial Lung Disease/Pneumonitis

RYBREVANT FASPRO can cause severe and fatal interstitial lung disease (ILD)/pneumonitis.

RYBREVANT FASPRO (Subcutaneous Amivantamab) with Lazertinib

In PALOMA-3 [see Adverse Reactions (6.1)], in 206 patients who received RYBREVANT FASPRO in combination with lazertinib, ILD/pneumonitis occurred in 6%, including Grade 3 in 1%, Grade 4 in 1.5%, and fatal cases in 1.9%. In total, 5% of patients permanently discontinued RYBREVANT FASPRO and lazertinib due to ILD/pneumonitis.

Intravenous Amivantamab with Lazertinib

In MARIPOSA [see Adverse Reactions (6.1)], in 421 patients who received intravenous amivantamab in combination with lazertinib, ILD/pneumonitis occurred in 3.1%, including Grade 3 in 1% and Grade 4 in 0.2% of patients. There was one fatal case of ILD/pneumonitis and 2.9% of patients permanently discontinued intravenous amivantamab and lazertinib due to ILD/pneumonitis.

Intravenous Amivantamab with Carboplatin and Pemetrexed

Based on the pooled safety population [see Adverse Reactions (6.1)], in 281 patients who received intravenous amivantamab in combination with carboplatin and pemetrexed, ILD/pneumonitis occurred in 2.1%, including 1.8% Grade 3 ILD/pneumonitis. Of these, 2.1% of patients permanently discontinued intravenous amivantamab due to ILD/pneumonitis.

Intravenous Amivantamab as a Single Agent

In CHRYSALIS [see Adverse Reactions (6.1)], in 302 patients who received intravenous amivantamab as a single agent, ILD/pneumonitis occurred in 3.3%, including 0.7% Grade 3. Three patients (1%) permanently discontinued intravenous amivantamab due to ILD/pneumonitis.

Monitor patients for new or worsening symptoms indicative of ILD/pneumonitis (e.g., dyspnea, cough, fever). Immediately withhold RYBREVANT FASPRO in patients with suspected ILD/pneumonitis and permanently discontinue if ILD/pneumonitis is confirmed [see Dosage and Administration (2.8)].

5.3 Venous Thromboembolic (VTE) Events with Concomitant Use with Lazertinib

RYBREVANT FASPRO in combination with lazertinib can cause serious and fatal venous thromboembolic (VTE) events, including deep vein thrombosis and pulmonary embolism. Without prophylactic anticoagulation, the majority of these events occurred during the first four months of therapy [see Adverse Reactions (6.1)].

RYBREVANT FASPRO (Subcutaneous Amivantamab) with Lazertinib

In PALOMA-3 [see Adverse Reactions (6.1)], in the 206 patients who received RYBREVANT FASPRO in combination with lazertinib, all Grade VTE occurred in 11% and 1.5% were Grade 3. Of the 206 patients treated with RYBREVANT FASPRO in combination with lazertinib, 80% received prophylactic anticoagulation at study entry. In the 164 patients treated with RYBREVANT FASPRO in combination with lazertinib who received prophylactic anticoagulation, all Grade VTE occurred in 7%. In the 42 patients treated with RYBREVANT FASPRO in combination with lazertinib who did not receive prophylactic anticoagulation, all Grade VTE occurred in 17%. In total, 0.5% of patients had VTE leading to dose reductions of RYBREVANT FASPRO and no patients required permanent discontinuation. The median time to onset of VTEs was 95 days (range: 17 to 390).

Intravenous Amivantamab with Lazertinib

In MARIPOSA [see Adverse Reactions (6.1)], in 421 patients who received intravenous amivantamab in combination with lazertinib, VTEs occurred in 36%, including Grade 3 in 10% and Grade 4 in 0.5% of patients. On-study VTEs occurred in 1.2% of patients (n=5) while receiving anticoagulation therapy. There were two fatal cases of VTE (0.5%), 9% of patients had VTE leading to dose interruptions of intravenous amivantamab, 1% of patients had VTE leading to dose reductions of intravenous amivantamab, and 3.1% of patients had VTE leading to permanent discontinuation of intravenous amivantamab. The median time to onset of VTEs was 84 days (range: 6 to 777).

Administer prophylactic anticoagulation for the first four months of treatment. The use of Vitamin K antagonists is not recommended.

Monitor for signs and symptoms of VTE events and treat as medically appropriate. Withhold RYBREVANT FASPRO and lazertinib based on severity [see Dosage and Administration (2.8)]. Once anticoagulant treatment has been initiated, resume RYBREVANT FASPRO and lazertinib at the same dose level at the discretion of the healthcare provider [see Dosage and Administration (2.8)]. In the event of VTE recurrence despite therapeutic anticoagulation, permanently discontinue RYBREVANT FASPRO. Treatment can continue with lazertinib at the same dose level at the discretion of the healthcare provider [see Dosage and Administration (2.8)]. Refer to the lazertinib prescribing information for recommended lazertinib dosage modification.

5.4 Dermatologic Adverse Reactions

RYBREVANT FASPRO can cause severe rash including toxic epidermal necrolysis (TEN), dermatitis acneiform, pruritus and dry skin.

RYBREVANT FASPRO (Subcutaneous Amivantamab) with Lazertinib

In PALOMA-3 [see Adverse Reactions (6.1)], in the 206 patients who received RYBREVANT FASPRO in combination with lazertinib, rash occurred in 80% of patients, including Grade 3 in 17% and Grade 4 in 0.5%. Rash leading to dose reduction occurred in 11% of patients, and RYBREVANT FASPRO was permanently discontinued due to rash in 1.5% of patients.

Intravenous Amivantamab with Lazertinib

In MARIPOSA [see Adverse Reactions (6.1)], in 421 patients who received intravenous amivantamab in combination with lazertinib, rash occurred in 86%, including 26% Grade 3. The median time to onset of rash was 14 days (range: 1 to 556 days). Rash leading to dose interruptions of intravenous amivantamab occurred in 37% of patients, rash leading to dose reductions of intravenous amivantamab occurred in 23% of patients, and rash leading to permanent discontinuation of intravenous amivantamab occurred in 5% of patients.

Intravenous Amivantamab with Carboplatin and Pemetrexed

Based on the pooled safety population [see Adverse Reactions (6.1)], in 281 patients who received intravenous amivantamab in combination with carboplatin and pemetrexed, rash occurred in 82%, including 15% Grade 3. Rash leading to dose reductions occurred in 14% of patients, and 2.5% permanently discontinued intravenous amivantamab and 3.1% discontinued pemetrexed.

Intravenous Amivantamab as a Single Agent

In CHRYSALIS [see Adverse Reactions (6.1)], in 302 patients who received intravenous amivantamab as a single agent, rash occurred in 74%, including 3.3% Grade 3. The median time to onset of rash was 14 days (range: 1 to 276 days). Rash leading to dose reduction occurred in 5% of patients, and intravenous amivantamab was permanently discontinued due to rash in 0.7% of patients. Toxic epidermal necrolysis (TEN) occurred in one patient (0.3%) treated with intravenous amivantamab as a single agent.

When initiating treatment with RYBREVANT FASPRO, prophylactic and concomitant medications are recommended to reduce the risk and severity of dermatologic adverse reactions [see Dosage and Administration (2.5)]. Instruct patients to limit sun exposure during and for 2 months after treatment with RYBREVANT FASPRO. Advise patients to wear protective clothing and use broad-spectrum UVA/UVB sunscreen.

If skin reactions develop, administer supportive care including topical corticosteroids and topical and/or oral antibiotics. For Grade 3 reactions, add oral steroids and consider dermatologic consultation. Promptly refer patients presenting with severe rash, atypical appearance or distribution, or lack of improvement within 2 weeks to a dermatologist. Withhold, dose reduce or permanently discontinue RYBREVANT FASPRO based on severity [see Dosage and Administration (2.8)].

5.5 Ocular Toxicity

RYBREVANT FASPRO can cause ocular toxicity including keratitis, blepharitis, dry eye symptoms, conjunctival redness, blurred vision, visual impairment, ocular itching, eye pruritus and uveitis.

RYBREVANT FASPRO (Subcutaneous Amivantamab) with Lazertinib

In PALOMA-3 [see Adverse Reactions (6.1)], in the 206 patients who received RYBREVANT FASPRO in combination with lazertinib, all Grade ocular toxicity occurred in 13%, including 0.5% Grade 3.

Intravenous Amivantamab with Lazertinib

In MARIPOSA [see Adverse Reactions (6.1)], in 421 patients treated with intravenous amivantamab in combination with lazertinib, ocular toxicity occurred in 16%, including 0.7% Grade 3 or 4 ocular toxicity.

Intravenous Amivantamab with Carboplatin and Pemetrexed

Based on the pooled safety population [see Adverse Reactions (6.1)], in 281 patients who received intravenous amivantamab in combination with carboplatin and pemetrexed, ocular toxicity occurred in 16%. All events were Grade 1 or 2.

Intravenous Amivantamab as a Single Agent

In CHRYSALIS [see Adverse Reactions (6.1)], in 302 patients treated with intravenous amivantamab, keratitis occurred in 0.7% and uveitis occurred in 0.3%. All events were Grade 1– 2.

Promptly refer patients presenting with new or worsening eye symptoms to an ophthalmologist. Withhold, dose reduce or permanently discontinue RYBREVANT FASPRO based on severity [see Dosage and Administration (2.8)].

5.6 Embryo-Fetal Toxicity

Based on its mechanism of action and findings from animal models, RYBREVANT FASPRO can cause fetal harm when administered to a pregnant woman. Administration of other EGFR inhibitor molecules to pregnant animals has resulted in an increased incidence of impairment of embryo-fetal development, embryo lethality, and abortion. Verify pregnancy status of females of reproductive potential prior to initiating RYBREVANT FASPRO. Advise pregnant women and females of reproductive potential of the potential risk to the fetus. Advise female patients of reproductive potential to use effective contraception during treatment and for 3 months after the last dose of RYBREVANT FASPRO [see Use in Specific Populations (8.1, 8.3)].

6 ADVERSE REACTIONS

The following adverse reactions are discussed elsewhere in the labeling:

- Hypersensitivity and Administration-Related Reactions [see Warnings and Precautions (5.1)]
- Interstitial Lung Disease/Pneumonitis [see Warnings and Precautions (5.2)]
- Venous Thromboembolic Events with Concomitant Use with Lazertinib [see Warnings and Precautions (5.3)]
- Dermatologic Adverse Reactions [see Warnings and Precautions (5.4)]
- Ocular Toxicity [see Warnings and Precautions (5.5)]

6.1 Clinical Trials Experience

Because clinical trials are conducted under widely varying conditions, adverse reaction rates observed in the clinical trials of a drug cannot be directly compared to rates in the clinical trials of another drug and may not reflect the rates observed in practice.

RYBREVANT FASPRO in Combination with Lazertinib

The safety population described in the WARNINGS AND PRECAUTIONS reflect exposure to RYBREVANT FASPRO in combination with lazertinib in 206 patients with previously treated locally advanced or metastatic NSCLC whose tumors have either an EGFR exon 19 deletion or an exon 21 L858R substitution mutation in PALOMA-3 [see Clinical Pharmacology (12.3)]. Patients received RYBREVANT FASPRO (N=206) or intravenous amivantamab (N=210), both in combination with lazertinib, at the recommended dosages until disease progression or unacceptable toxicity. Among 206 patients who received RYBREVANT FASPRO in combination with lazertinib, 47% were exposed for 6 months or longer and 12% were exposed for greater than one year. The most common adverse reactions (≥ 20%) were rash, nail toxicity, musculoskeletal pain, fatigue, stomatitis, edema, nausea, diarrhea, vomiting, constipation, decreased appetite, and headache. The most common Grade 3 or 4 laboratory abnormalities (≥ 2%) were decreased lymphocyte count, decreased sodium, decreased potassium, decreased albumin, increased alanine aminotransferase, increased aspartate aminotransferase, decreased platelet count, increased gamma-glutamyl transferase, and decreased hemoglobin.

Intravenous Amivantamab in Combination with Lazertinib

The data described in the WARNINGS AND PRECAUTIONS also reflect exposure to intravenous amivantamab in combination with lazertinib in the MARIPOSA study in 421 patients with previously untreated locally advanced or metastatic NSCLC whose tumors have EGFR exon 19 deletions or exon 21 L858R substitution mutations [see Clinical Studies (14.1)]. Patients received intravenous amivantamab at 1,050 mg (for patients < 80 kg) or 1,400 mg (for patients ≥ 80 kg) once weekly for 4 weeks, then every 2 weeks thereafter starting at week 5 in combination with lazertinib, 240 mg orally once daily, until disease progression or unacceptable toxicity. Among 421 patients who received intravenous amivantamab in combination with lazertinib, 73% were exposed for 6 months or longer and 59% were exposed for greater than one year. The most common adverse reactions (≥ 20%) were rash, nail toxicity, infusion-related reaction, musculoskeletal pain, stomatitis, edema, VTE, paresthesia, fatigue, diarrhea, constipation, COVID-19, hemorrhage, dry skin, decreased appetite, pruritus, and nausea. The most common Grade 3 or 4 laboratory abnormalities (≥ 2%) were decreased albumin, decreased sodium, increased ALT, decreased potassium, decreased hemoglobin, increased AST, increased GGT, and increased magnesium.

Intravenous Amivantamab in Combination with Carboplatin and Pemetrexed

The pooled safety population described in the WARNINGS AND PRECAUTIONS also reflect exposure to intravenous amivantamab in combination with carboplatin and pemetrexed in 281 patients in two studies:

MARIPOSA-2 [see Clinical Studies (14.2)] in 130 patients with previously treated locally advanced or metastatic NSCLC with EGFR exon 19 deletions or exon 21 L858R substitution mutations whose disease has progressed on or after treatment with osimertinib.
PAPILLON [see Clinical Studies (14.3)] in 151 patients with previously untreated, locally advanced or metastatic NSCLC with EGFR exon 20 insertion mutations.

Patients received intravenous amivantamab at 1,400 mg (for patients < 80 kg) or 1,750 mg (for patients ≥ 80 kg) once weekly through 4 weeks, then every 3 weeks with a dose of 1,750 mg (for patients < 80 kg) or 2,100 mg (for patients ≥ 80 kg) starting at Week 7 until disease progression or unacceptable toxicity, in combination with carboplatin at area under the curve AUC 5 once every 3 weeks, for up to 12 weeks, and pemetrexed at 500 mg/m^2 once every 3 weeks until disease progression or unacceptable toxicity. Among 281 patients who received intravenous amivantamab in combination with carboplatin and pemetrexed, 65% were exposed for 6 months or longer and 24% were exposed for greater than one year. In the safety population, the most common (≥ 20%) adverse reactions were rash, nail toxicity, infusion-related reaction, fatigue, nausea, stomatitis, constipation, edema, decreased appetite, musculoskeletal pain, vomiting, and COVID-19. The most common Grade 3 to 4 laboratory abnormalities (≥ 2%) were decreased neutrophils, decreased leukocytes, decreased platelets, decreased hemoglobin, decreased potassium, decreased sodium, increased alanine aminotransferase, increased gamma-glutamyl transferase, and decreased albumin.

Intravenous Amivantamab as a Single Agent

The pooled safety population described in the WARNINGS AND PRECAUTIONS also reflect exposure to intravenous amivantamab as a single agent in CHRYSALIS [see Clinical Studies (14.4)] in 302 patients with locally advanced or metastatic NSCLC. Patients received intravenous amivantamab at 1,050 mg (for patient baseline body weight < 80 kg) or 1,400 mg (for patient baseline body weight ≥ 80 kg) once weekly for 4 weeks, then every 2 weeks thereafter until disease progression or unacceptable toxicity. Among 302 patients who received intravenous amivantamab as a single agent, 36% were exposed for 6 months or longer and 12% were exposed for greater than one year. In the safety population, the most common (≥ 20%) adverse reactions were rash, infusion-related reaction, paronychia, musculoskeletal pain, dyspnea, nausea, edema, cough, fatigue, stomatitis, constipation, vomiting and pruritus. The most common Grade 3 to 4 laboratory abnormalities (≥ 2%) were increased gamma-glutamyl transferase, decreased sodium, decreased potassium and increased alkaline phosphatase.

Subcutaneous RYBREVANT FASPRO

Previously Treated NSCLC with EGFR Exon 19 Deletions or Exon 21 L858R Substitution Mutations – RYBREVANT FASPRO In Combination with Lazertinib

PALOMA-3 (Every 2-week dosing)

The safety of RYBREVANT FASPRO in combination with lazertinib was evaluated in the PALOMA-3 study [see Clinical Pharmacology (12.3)]. Eligible patients were required to have locally advanced or metastatic NSCLC whose tumors have either an EGFR exon 19 deletion or an exon 21 L858R substitution mutation and whose disease has progressed on prior treatment with osimertinib and platinum-based chemotherapy. Patients were randomized to receive lazertinib 240 mg orally once daily in combination with either RYBREVANT FASPRO (N=206) or intravenous amivantamab (N=210) at the recommended dosages until disease progression or unacceptable toxicity. In total, 164 patients (80%) receiving RYBREVANT FASPRO and 171 patients (81%) receiving intravenous amivantamab received prophylactic anticoagulants with a direct oral anticoagulant or low molecular weight heparin during the first four months of study treatment. Among patients receiving RYBREVANT FASPRO, 47% were exposed for ≥ 6 months and 12% were exposed for ≥ 1 year.

The median age of patients who received RYBREVANT FASPRO was 61 years (range: 35–82); 67% were female; 61% Asian, 38% White, 0.5% Black, and 0.5% did not report race; 6% were Hispanic or Latino.

Serious adverse reactions occurred in 33% of patients who received RYBREVANT FASPRO in combination with lazertinib. Serious adverse reactions in ≥ 2% of patients who received RYBREVANT FASPRO in combination with lazertinib included ILD/pneumonitis (6%); and pneumonia, VTE and fatigue (2.4% each). Death due to adverse reactions occurred in 5% of patients treated with RYBREVANT FASPRO, including ILD/pneumonitis (1.9%), pneumonia (1.5%), and respiratory failure and sudden death (1% each).

Permanent discontinuations of RYBREVANT FASPRO due to an adverse reaction occurred in 13% of patients. Adverse reactions leading to RYBREVANT FASPRO discontinuation in ≥ 1% of patients were ILD/pneumonitis (5%), rash (1.9%) and pneumonia 1%.

Dosage interruptions of RYBREVANT FASPRO due to an adverse reaction occurred in 54% of patients. Adverse reactions requiring RYBREVANT FASPRO dose interruption in ≥ 5% of patients were rash (21%) and nail toxicity (13%).

Dose reductions of RYBREVANT FASPRO due to an adverse reaction occurred in 20% of patients. Adverse reactions requiring RYBREVANT FASPRO dose reductions in ≥ 5% of patients were rash (11%) and nail toxicity (8%).

Table 10 summarizes the adverse reactions (≥ 10%) in PALOMA-3.

Table 10: Adverse Reactions (≥ 10%) in Patients with Previously Treated NSCLC with EGFR Exon 19 Deletions or Exon 21 L858R Substitution Mutations Who Received RYBREVANT FASPRO in Combination with Lazertinib in PALOMA-3
Adverse Reaction | RYBREVANT FASPRO with lazertinib (N=206) |  | Intravenous amivantamab with lazertinib (N=210)
Adverse Reaction | All Grades (%) | Grades 3 or 4 (%) | All Grades (%) | Grades 3 or 4 (%)
Skin and subcutaneous tissue disorders
Rash [Grouped terms] | 80 | 17 | 78 | 13
Nail toxicity | 58 | 3.9 | 56 | 2.9
Dry skin | 18 | 0 | 18 | 0
Pruritus | 17 | 0 | 12 | 0
Musculoskeletal and connective tissue disorders
Musculoskeletal pain | 50 | 2.4 | 35 | 3.8
General disorders and administration site conditions
Fatigue | 37 | 3.4 | 31 | 2.4
Edema | 34 | 2.9 | 34 | 1
Pyrexia | 13 | 0 | 11 | 0
Local injection site reactions | 11 | 0 | 0 | 0
Gastrointestinal disorders
Stomatitis | 36 | 0.5 | 38 | 2.9
Nausea | 30 | 0.5 | 25 | 1.4
Diarrhea | 22 | 1.5 | 19 | 1
Vomiting | 22 | 1 | 20 | 0.5
Constipation | 22 | 0 | 20 | 0.5
Metabolism and nutrition disorders
Decreased appetite | 22 | 0.5 | 25 | 1.4
Nervous system disorders
Headache | 21 | 0.5 | 19 | 0.5
Peripheral neuropathy | 19 | 1.5 | 23 | 1.4
Dizziness | 12 | 0 | 12 | 0
Injury, poisoning and procedural complications
Administration-related reactions | 13 | 0.5 | 66 | 3.8
Eye disorders
Ocular toxicity | 13 | 0.5 | 11 | 0.5
Vascular disorders
Venous thromboembolism | 11 | 1.5 | 18 | 5

Clinically relevant adverse reactions in < 10% of patients who received RYBREVANT FASPRO in combination with lazertinib not included in the table above were abdominal pain, hemorrhoids, ILD/pneumonitis, and skin ulcer.

Table 11 summarizes the laboratory abnormalities in PALOMA-3.

Table 11: Select Laboratory Abnormalities (≥ 20%) that Worsened from Baseline in Patients with NSCLC with EGFR Exon 19 Deletions or Exon 21 L858R Substitution Mutations in PALOMA-3 [The denominator used to calculate the rate is the number of patients with a baseline value and at least one post-treatment value for the specific lab test.]
Laboratory Abnormality | RYBREVANT FASPRO with lazertinib (N=206) |  | Intravenous amivantamab with lazertinib (N=210)
Laboratory Abnormality | All Grades (%) | Grades 3 or 4 (%) | All Grades (%) | Grades 3 or 4 (%)
Chemistry
Decreased Albumin | 92 | 4.9 | 91 | 5
Increased Alkaline Phosphatase | 47 | 1.5 | 37 | 0
Increased Alanine Aminotransferase | 45 | 3.4 | 50 | 5
Decreased Sodium | 36 | 5 | 43 | 8
Increased Aspartate Aminotransferase | 36 | 2 | 40 | 2.4
Decreased Calcium (Corrected) | 33 | 0 | 36 | 0
Decreased Magnesium | 27 | 0 | 30 | 1.4
Increased Gamma-Glutamyl Transferase | 26 | 2 | 27 | 1.9
Decreased Potassium | 22 | 5 | 25 | 4.3
Hematology
Decreased Lymphocyte Count | 57 | 6 | 60 | 29
Decreased Platelet Count | 37 | 2.4 | 42 | 1.9
Decreased White Blood Cell | 36 | 0.5 | 31 | 0.5
Decreased Hemoglobin | 34 | 2 | 36 | 2.4

Clinical Trials Experience of Amivantamab Intravenous Formulation

Below is a description of adverse reactions of intravenous amivantamab in these adequate and well-controlled NSCLC studies.

First-line Treatment of NSCLC with Exon 19 Deletions or Exon 21 L858R Substitution Mutations – Intravenous Amivantamab in Combination with Lazertinib

MARIPOSA

The safety data described below reflect exposure to intravenous amivantamab in combination with lazertinib in 421 previously untreated patients with locally advanced or metastatic NSCLC whose tumors have EGFR exon 19 deletions or exon 21 L858R substitution mutation in the MARIPOSA [see Clinical Studies (14.1)]. Patients received intravenous amivantamab at 1,050 mg (for patients < 80 kg) or 1,400 mg (for patients ≥ 80 kg) once weekly for 4 weeks, then every 2 weeks thereafter starting at week 5 in combination with lazertinib, 240 mg orally once daily. Among the 421 patients who received intravenous amivantamab in combination with lazertinib, 73% were exposed to intravenous amivantamab for ≥ 6 months and 59% were exposed to intravenous amivantamab for > 1 year.

The median age of patients who received intravenous amivantamab in combination with lazertinib was 64 years (range: 25 to 88); 64% were female; 59% were Asian, 38% were White, 1.7% were American Indian or Alaska Native, 0.7% were Black or African American, 1% were of unknown or other races; and 13% were Hispanic or Latino, 67% had Eastern Cooperative Oncology Group (ECOG) performance status (PS) of 1, 33% had ECOG PS of 0, 60% had EGFR exon 19 deletions, and 40% had EGFR exon 21 L858R substitution mutations.

Serious adverse reactions occurred in 49% of patients who received intravenous amivantamab in combination with lazertinib. Serious adverse reactions occurring in ≥ 2% of patients included VTE (11%), pneumonia (4%), rash, and ILD/pneumonitis (2.9% each), COVID-19 (2.4%), pleural effusion and infusion-related reaction (2.1% each). Fatal adverse reactions occurred in 7% of patients who received intravenous amivantamab in combination with lazertinib due to death not otherwise specified (1.2%); sepsis and respiratory failure (1% each); pneumonia, myocardial infarction and sudden death (0.7% each); cerebral infarction, pulmonary embolism (PE), and COVID-19 infection (0.5% each); and ILD/pneumonitis, acute respiratory distress syndrome (ARDS), and cardiopulmonary arrest (0.2% each).

Permanent discontinuation of intravenous amivantamab due to an adverse reaction occurred in 34% of patients. Adverse reactions which resulted in permanent discontinuation in ≥ 1% of patients included rash, infusion-related reactions, nail toxicity, VTE, ILD/pneumonitis, pneumonia, edema, hypoalbuminemia, fatigue, paresthesia and dyspnea.

Dosage interruption of intravenous amivantamab due to an adverse reaction occurred in 88% of patients. Adverse reactions which required dosage interruption in ≥ 5% of patients were infusion-related reactions, rash, nail toxicity, COVID-19, VTE, increased ALT, edema, and hypoalbuminemia.

Dose reductions of intravenous amivantamab due to an adverse reaction occurred in 46% of patients. Adverse reactions requiring dose reductions in ≥ 5% of patients were rash and nail toxicity.

The most common adverse reactions (≥ 20%) were rash, nail toxicity, infusion-related reaction, musculoskeletal pain, stomatitis, edema, VTE, paresthesia, fatigue, diarrhea, constipation, COVID-19, hemorrhage, dry skin, decreased appetite, pruritus, and nausea. The most common Grade 3 or 4 laboratory abnormalities (≥ 2%) were decreased albumin, decreased sodium, increased ALT, decreased potassium, decreased hemoglobin, increased AST, increased GGT, and increased magnesium.

Table 12 summarizes the adverse reactions (≥ 10%) in MARIPOSA.

Table 12: Adverse Reactions (≥ 10%) in Patients with NSCLC with Exon 19 Deletion or Exon 21 L858R Substitution Mutations in MARIPOSA
Adverse Reaction | Intravenous amivantamab in combination with lazertinib (N=421) |  | Osimertinib (N=428)
Adverse Reaction | All Grades (%) | Grade 3 or 4 (%) | All Grades (%) | Grade 3 or 4 (%)
Skin and subcutaneous tissue disorders
Rash [Grouped terms] | 86 | 26 | 48 | 1.2
Nail toxicity | 71 | 11 | 34 | 0.7
Dry skin | 25 | 1 | 18 | 0.2
Pruritus | 24 | 0.5 | 17 | 0.2
Injury, poisoning and procedural complications
Infusion-related reaction [Applicable for intravenous amivantamab only] | 63 | 6 | 0 | 0
Musculoskeletal and connective tissue disorders
Musculoskeletal pain | 47 | 2.1 | 39 | 1.9
Gastrointestinal disorders
Stomatitis | 43 | 2.4 | 27 | 0.5
Diarrhea | 31 | 2.6 | 45 | 0.9
Constipation | 29 | 0 | 13 | 0
Nausea | 21 | 1.2 | 14 | 0.2
Vomiting | 12 | 0.5 | 5 | 0
Abdominal pain | 11 | 0 | 10 | 0
Hemorrhoids | 10 | 0.2 | 2.1 | 0.2
General disorders and administration site conditions
Edema | 43 | 2.6 | 8 | 0
Fatigue | 32 | 3.8 | 20 | 1.9
Pyrexia | 12 | 0 | 9 | 0
Vascular disorders
Venous thromboembolism | 36 | 11 | 8 | 2.8
Hemorrhage | 25 | 1 | 13 | 1.2
Nervous system disorders
Paresthesia | 35 | 1.7 | 10 | 0.2
Dizziness | 14 | 0 | 10 | 0
Headache | 13 | 0.2 | 13 | 0
Infections and infestations
COVID-19 | 26 | 1.7 | 24 | 1.4
Conjunctivitis | 11 | 0.2 | 1.6 | 0
Metabolism and nutrition disorders
Decreased appetite | 24 | 1 | 18 | 1.4
Respiratory, thoracic, and mediastinal disorders
Cough | 19 | 0 | 23 | 0
Dyspnea | 14 | 1.7 | 17 | 3.5
Eye disorders
Ocular toxicity | 16 | 0.7 | 7 | 0
Psychiatric disorders
Insomnia | 10 | 0 | 11 | 0

Clinically relevant adverse reactions in < 10% of patients who received intravenous amivantamab in combination with lazertinib included skin ulcer and ILD/pneumonitis.

Table 13 summarizes the laboratory abnormalities in MARIPOSA.

Table 13: Select Laboratory Abnormalities (≥ 20%) That Worsened from Baseline in Patients with NSCLC with EGFR Exon 19 Deletion or Exon 21 L858R Substitution Mutations in MARIPOSA [The denominator used to calculate the rate is the number of patients with a baseline value and at least one post-treatment value for the specific lab test.]
 | Intravenous amivantamab in combination with lazertinib (N=421) |  | Osimertinib (N=428)
Laboratory Abnormality | All Grades (%) | Grade 3 or 4 (%) | All Grades (%) | Grade 3 or 4 (%)
Chemistry
Decreased albumin | 89 | 8 | 22 | 0.2
Increased ALT | 65 | 7 | 29 | 2.6
Increased AST | 52 | 3.8 | 36 | 1.9
Increased alkaline phosphatase | 45 | 0.5 | 15 | 0.5
Decreased calcium (corrected) | 41 | 1.4 | 27 | 0.7
Increased GGT | 39 | 2.6 | 24 | 1.9
Decreased sodium | 38 | 7 | 35 | 5
Decreased potassium | 30 | 5 | 15 | 1.2
Increased creatinine | 26 | 0.7 | 35 | 0.7
Decreased magnesium | 25 | 0.7 | 10 | 0.2
Increased magnesium | 12 | 2.6 | 20 | 4.8
Hematology
Decreased platelet count | 52 | 0.7 | 57 | 1.4
Decreased hemoglobin | 47 | 3.8 | 56 | 1.9
Decreased white blood cell | 38 | 1 | 66 | 0.7
Decreased neutrophils | 15 | 1.4 | 33 | 1.4

Previously Treated NSCLC with EGFR Exon 19 Deletions or Exon 21 L858R Substitution Mutations – Intravenous Amivantamab in Combination with Carboplatin and Pemetrexed

MARIPOSA-2

The safety data described below reflect exposure to intravenous amivantamab in combination with carboplatin and pemetrexed was evaluated in MARIPOSA-2 [see Clinical Studies (14.2)]. Eligible patients had locally advanced or metastatic NSCLC with EGFR exon 19 deletions or exon 21 L858R substitution mutations with progressive disease on or after treatment with osimertinib. Patients with asymptomatic or previously treated and stable intracranial metastases were eligible. Patients received intravenous amivantamab at 1,400 mg (for patients < 80 kg) or 1,750 mg (for patients ≥ 80 kg) once weekly through 4 weeks, then every 3 weeks with a dose of 1,750 mg (for patients < 80 kg) or 2,100 mg (for patients ≥ 80 kg) starting at Week 7 until disease progression or unacceptable toxicity, in combination with carboplatin at area under the curve AUC 5 once every 3 weeks, for up to 12 weeks, and pemetrexed at 500 mg/m^2 once every 3 weeks until disease progression or unacceptable toxicity. Among patients who received intravenous amivantamab (n=130), 52% were exposed for 6 months or longer and 7% were exposed for greater than one year. The median treatment duration was 6.3 months (range: 0 to 14.7 months).

The median age was 62 years (range: 36 to 84 years); 62% were female; 48% were Asian, 46% were White, 2.3% Black or African American, 1.5% race not reported, 1.5% race unknown, 0.8% Alaska native; 7% were Hispanic or Latino; and 87% had baseline body weight < 80 kg.

Serious adverse reactions occurred in 32% of patients who received intravenous amivantamab in combination with carboplatin and pemetrexed. Serious adverse reactions in > 2% of patients included dyspnea (3.1%), thrombocytopenia (3.1%), sepsis (2.3%), and pulmonary embolism (2.3%). Fatal adverse reactions occurred in 2.3% of patients who received intravenous amivantamab in combination with carboplatin and pemetrexed; these included respiratory failure, sepsis, and ventricular fibrillation (0.8% each).

Permanent discontinuation of intravenous amivantamab due to adverse reactions occurred in 11% of patients. The most frequent adverse reactions leading to discontinuation of intravenous amivantamab in ≥ 5% of patients were infusion-related reactions.

Dose interruptions of intravenous amivantamab due to an adverse reaction occurred in 60% of patients. Infusion-related reactions (IRR) requiring infusion interruptions occurred in 52% of patients. Adverse reactions requiring dose interruption in ≥ 5% of patients included infusion-related reaction, rash and fatigue.

Dose reductions of intravenous amivantamab due to an adverse reaction occurred in 17% of patients. Adverse reactions requiring dose reductions in ≥ 2% of patients included rash.

The most common adverse reactions ≥ 20% were rash, infusion-related reactions, fatigue, nail toxicity, nausea, constipation, edema, stomatitis, decreased appetite, musculoskeletal pain, vomiting, and COVID-19.

Table 14 summarizes the adverse reactions in MARIPOSA-2.

Table 14: Adverse Reactions (≥ 10%) in Previously Treated Patients with NSCLC with EGFR Exon 19 Deletions or Exon 21 L858R Substitution Mutations Treated with Intravenous Amivantamab in Combination with Carboplatin and Pemetrexed in MARIPOSA-2
 | Intravenous Amivantamab With Carboplatin and Pemetrexed (N=130) |  | Carboplatin and Pemetrexed (N=243)
Adverse Reaction | All Grades (%) | Grade 3 or 4 (%) | All Grades (%) | Grade 3 or 4 (%)
Skin and subcutaneous tissue disorders
Rash [Grouped term] | 72 | 11 | 12 | 0
Nail toxicity | 45 | 2.3 | 0.4 | 0
Pruritus | 15 | 0 | 7 | 0
Dry skin | 15 | 0 | 2.5 | 0
General disorders and administration site conditions
Infusion-related reaction | 59 | 5.4 | 0.4 | 0
Fatigue | 51 | 3.8 | 35 | 3.7
Edema | 36 | 1.5 | 11 | 0.4
Pyrexia | 12 | 0 | 10 | 0
Gastrointestinal disorders
Nausea | 45 | 0.8 | 37 | 0.8
Constipation | 39 | 0.8 | 30 | 0
Stomatitis | 35 | 2.3 | 11 | 0
Vomiting | 25 | 0.8 | 17 | 0.4
Diarrhea | 15 | 1.5 | 7 | 0.8
Metabolism and nutrition disorders
Decreased appetite | 31 | 0 | 21 | 1.2
Musculoskeletal and connective tissue disorders
Musculoskeletal pain | 30 | 3.1 | 19 | 0.8
Infections and infestations
COVID-19 | 21 | 1.5 | 10 | 0
Eye disorders
Ocular toxicity | 17 | 0 | 3.7 | 0
Vascular disorders
Hemorrhage | 14 | 0.8 | 4.9 | 0
Venous Thromboembolism (VTE) | 10 | 2.3 | 4.5 | 2.9
Respiratory, thoracic, and mediastinal disorders
Cough | 14 | 0 | 16 | 0.4
Dyspnea | 13 | 1.5 | 8 | 1.2

Clinically relevant adverse reactions in < 10% of patients who received intravenous amivantamab in combination with carboplatin and pemetrexed include: abdominal pain, hemorrhoids, dizziness, visual impairment, trichomegaly, keratitis, interstitial lung disease, and skin ulcer.

Table 15 summarizes the laboratory abnormalities in MARIPOSA-2.

Table 15: Select Laboratory Abnormalities (≥ 20%) That Worsened from Baseline in Patients with NSCLC with EGFR Exon 19 Deletions or Exon 21 L858R Substitution Mutations Treated with Intravenous Amivantamab in Combination with Carboplatin and Pemetrexed in MARIPOSA-2
 | Intravenous Amivantamab with Carboplatin and Pemetrexed (N=130) |  | Carboplatin and Pemetrexed (N=243)
Laboratory Abnormality | All Grades (%) | Grade 3 or 4 (%) | All Grades (%) | Grade 3 or 4 (%)
Hematology
Decreased white blood cells | 91 | 42 | 85 | 19
Decreased neutrophils | 74 | 49 | 64 | 25
Decreased platelets | 74 | 17 | 58 | 9
Decreased hemoglobin | 71 | 12 | 77 | 9
Decreased lymphocytes | 69 | 28 | 58 | 18
Chemistry
Decreased albumin | 73 | 3.8 | 26 | 0.4
Decreased sodium | 49 | 11 | 30 | 6
Increased aspartate aminotransferase | 47 | 0.8 | 52 | 0.9
Increased alkaline phosphatase | 42 | 0 | 29 | 0.4
Increased alanine aminotransferase | 39 | 3.9 | 56 | 6
Decreased magnesium | 38 | 0.8 | 17 | 0.4
Decreased potassium | 37 | 11 | 12 | 3.4
Increased gamma-glutamyl transferase | 30 | 3.1 | 41 | 1.3
Decreased calcium (corrected) | 25 | 0 | 11 | 0.9

First-Line Treatment of NSCLC with EGFR Exon 20 Insertion Mutations – Intravenous Amivantamab in Combination with Carboplatin and Pemetrexed

PAPILLON

The safety data described below reflect exposure to intravenous amivantamab in combination with carboplatin and pemetrexed at the recommended dosage in the PAPILLON trial [see Clinical Studies (14.3)] in 151 patients with locally advanced or metastatic NSCLC with EGFR exon 20 insertion mutations. Among patients who received intravenous amivantamab in combination with carboplatin and pemetrexed the median exposure was 9.7 months (range: 0.0 to 26.9 months). In patients that received carboplatin and pemetrexed alone, the median exposure was 6.7 months (range 0.0 to 25.3).

The median age was 61 years (range: 27 to 86 years); 56% were female; 64% were Asian, 32% were White, 1.3% were Black or African American, race was not reported in 1.3% of patients; 89% were not Hispanic or Latino; 86% had baseline body weight < 80 kg.

Serious adverse reactions occurred in 37% of patients who received intravenous amivantamab in combination with carboplatin and pemetrexed. Serious adverse reactions in ≥ 2% of patients included rash, pneumonia, interstitial lung disease (ILD), pulmonary embolism, vomiting, and COVID-19. Fatal adverse reactions occurred in 7 patients (4.6%) due to pneumonia, cerebrovascular accident, cardio-respiratory arrest, COVID-19, sepsis, and death not otherwise specified.

Permanent discontinuation of intravenous amivantamab due to an adverse reaction occurred in 11% of patients. Adverse reactions resulting in permanent discontinuation of intravenous amivantamab in ≥ 1% of patients were rash and ILD.

Dose interruptions of intravenous amivantamab due to an adverse reaction occurred in 64% of patients. Infusion-related reactions (IRR) requiring infusion interruptions occurred in 38% of patients. Adverse reactions requiring dose interruption in ≥ 5% of patients included rash and nail toxicity.

Dose reductions of intravenous amivantamab due to an adverse reaction occurred in 36% of patients. Adverse reactions requiring dose reductions in ≥ 5% of patients included rash and nail toxicity.

The most common adverse reactions (≥ 20%) were rash, nail toxicity, stomatitis, infusion-related reaction, fatigue, edema, constipation, decreased appetite, nausea, COVID-19, diarrhea, and vomiting. The most common Grade 3 to 4 laboratory abnormalities (≥ 2%) were decreased albumin, increased alanine aminotransferase, increased gamma-glutamyl transferase, decreased sodium, decreased potassium, decreased magnesium, and decreases in white blood cells, hemoglobin, neutrophils, platelets, and lymphocytes.

Table 16 summarizes the adverse reactions in PAPILLON.

Table 16: Adverse Reactions (≥ 10%) in Patients with Metastatic NSCLC with Exon 20 Insertion Mutations Who Received Intravenous Amivantamab in Combination with Carboplatin and Pemetrexed in PAPILLON
 | Intravenous Amivantamab in Combination with Carboplatin and Pemetrexed (N=151) |  | Carboplatin and Pemetrexed (N=155)
Adverse Reaction [Adverse reactions were graded using CTCAE version 5.0] | All Grades (%) | Grade 3 or 4 (%) | All Grades (%) | Grade 3 or 4 (%)
Skin and subcutaneous tissue disorders
Rash [Grouped Term] | 90 | 19 | 19 | 0
Nail toxicity | 62 | 7 | 3 | 0
Dry skin | 17 | 0 | 6 | 0
Gastrointestinal disorders
Stomatitis | 43 | 4 | 11 | 0
Constipation | 40 | 0 | 30 | 0.7
Nausea | 36 | 0.7 | 42 | 0
Vomiting | 21 | 3.3 | 19 | 0.7
Diarrhea | 21 | 3 | 13 | 1.3
Hemorrhoids | 12 | 1 | 1.3 | 0
Abdominal pain | 11 | 0.7 | 8 | 0
General disorders and administration site conditions
Infusion-related reaction | 42 | 1.3 | 1.3 | 0
Fatigue | 42 | 6 | 45 | 3.9
Edema | 40 | 1.3 | 19 | 0
Pyrexia | 17 | 0 | 6 | 0
Metabolism and nutrition disorders
Decreased appetite | 36 | 2.6 | 28 | 1.3
Infections and infestations
COVID-19 | 24 | 2 | 14 | 0.6
Pneumonia | 13 | 5 | 6 | 1.9
Vascular disorders
Hemorrhage | 18 | 0.7 | 11 | 1.9
Respiratory, thoracic, and mediastinal disorders
Cough | 17 | 0 | 16 | 0
Dyspnea | 11 | 1.3 | 16 | 3.2
Investigations
Weight decreased | 14 | 0.7 | 8 | 0
Nervous system disorders
Dizziness | 11 | 0 | 12 | 0
Psychiatric disorders
Insomnia | 11 | 0 | 13 | 0

Clinically relevant adverse reactions in < 10% of patients who received intravenous amivantamab in combination with carboplatin and pemetrexed included pulmonary embolism, deep vein thrombosis, skin ulcer, conjunctivitis, and interstitial lung disease (ILD)/pneumonitis.

Table 17 summarizes the laboratory abnormalities in PAPILLON.

Table 17: Select Laboratory Abnormalities (≥ 20%) That Worsened from Baseline in Patients with Metastatic NSCLC with EGFR Exon 20 Insertion Mutations Who Received Intravenous Amivantamab in Combination with Carboplatin and Pemetrexed in PAPILLON
 | Intravenous Amivantamab in Combination with Carboplatin and Pemetrexed [The denominator used to calculate the rate varied from 113 to 150 based on the number of patients with a baseline value and at least one post-treatment value.] |  | Carboplatin in Combination with Pemetrexed [The denominator used to calculate the rate varied from 119 to 154 based on the number of patients with a baseline value and at least one post-treatment value.]
Laboratory Abnormality [Adverse reactions were graded using CTCAE version 5.0] | All Grades (%) | Grade 3 or 4 (%) | All Grades (%) | Grade 3 or 4 (%)
Hematology
Decreased white blood cells | 89 | 17 | 76 | 10
Decreased hemoglobin | 79 | 11 | 85 | 13
Decreased neutrophils | 76 | 36 | 61 | 23
Decreased platelets | 70 | 10 | 54 | 12
Decreased lymphocytes | 61 | 11 | 49 | 13
Chemistry
Decreased albumin | 87 | 7 | 34 | 1
Increased aspartate aminotransferase | 60 | 1 | 61 | 1
Increased alanine aminotransferase | 57 | 4 | 54 | 1
Decreased sodium | 55 | 7 | 39 | 4
Increased alkaline phosphatase | 51 | 1 | 28 | 0
Decreased potassium | 44 | 11 | 17 | 1
Decreased magnesium | 39 | 2 | 30 | 1
Increased gamma-glutamyl transferase | 38 | 4 | 43 | 4
Decreased calcium (corrected) | 27 | 1 | 18 | 1

Previously Treated NSCLC with EGFR Exon 20 Insertion Mutations – Intravenous Amivantamab as a Single Agent

CHRYSALIS

The safety data described below reflect exposure to intravenous amivantamab at the recommended dosage in 129 patients with locally advanced or metastatic NSCLC with EGFR exon 20 insertion mutations in the CHRYSALIS trial [see Clinical Studies (14.4)], whose disease had progressed on or after platinum-based chemotherapy. Patients received intravenous amivantamab at 1,050 mg (for patient baseline body weight < 80 kg) or 1,400 mg (for patient baseline body weight ≥ 80 kg) once weekly for 4 weeks, then every 2 weeks thereafter until disease progression or unacceptable toxicity. Among patients who received intravenous amivantamab, 44% were exposed for 6 months or longer and 12% were exposed for greater than one year.

The median age was 62 years (range: 36 to 84 years); 61% were female; 55% were Asian, 35% were White, and 2.3% were Black; and 82% had baseline body weight < 80 kg.

Serious adverse reactions occurred in 30% of patients who received intravenous amivantamab. Serious adverse reactions in ≥ 2% of patients included pulmonary embolism, pneumonitis/ILD, dyspnea, musculoskeletal pain, pneumonia, and muscular weakness. Fatal adverse reactions occurred in 2 patients (1.5%) due to pneumonia and 1 patient (0.8%) due to sudden death.

Permanent discontinuation of intravenous amivantamab due to an adverse reaction occurred in 11% of patients. Adverse reactions resulting in permanent discontinuation of intravenous amivantamab in ≥ 1% of patients were pneumonia, IRR, pneumonitis/ILD, dyspnea, pleural effusion, and rash.

Dose interruptions of intravenous amivantamab due to an adverse reaction occurred in 78% of patients. Infusion-related reactions (IRR) requiring infusion interruptions occurred in 59% of patients. Adverse reactions requiring dose interruption in ≥ 5% of patients included dyspnea, nausea, rash, vomiting, fatigue, and diarrhea.

Dose reductions of intravenous amivantamab due to an adverse reaction occurred in 15% of patients. Adverse reactions requiring dose reductions in ≥ 2% of patients included rash and paronychia.

The most common adverse reactions (≥ 20%) were rash, IRR, paronychia, musculoskeletal pain, dyspnea, nausea, fatigue, edema, stomatitis, cough, constipation, and vomiting. The most common Grade 3 to 4 laboratory abnormalities (≥ 2%) were decreased lymphocytes, decreased albumin, decreased phosphate, decreased potassium, increased glucose, increased alkaline phosphatase, increased gamma-glutamyl transferase, and decreased sodium.

Table 18 summarizes the adverse reactions in CHRYSALIS.

Table 18: Adverse Reactions (≥ 10%) in Patients with NSCLC with Exon 20 Insertion Mutations Whose Disease Has Progressed on or after Platinum-based Chemotherapy and Received Intravenous Amivantamab in CHRYSALIS
Adverse Reactions | Intravenous Amivantamab [Adverse reactions were graded using CTCAE version 4.03] (N=129)
Adverse Reactions | All Grades (%) | Grades 3 or 4 (%)
Skin and subcutaneous tissue disorders
Rash [Grouped term] | 84 | 3.9
Pruritus | 18 | 0
Dry skin | 14 | 0
General disorders and administration site conditions
Infusion-related reaction | 64 | 3.1
Fatigue | 33 | 2.3
Edema | 27 | 0.8
Pyrexia | 13 | 0
Infections and infestations
Paronychia | 50 | 3.1
Pneumonia | 10 | 0.8
Musculoskeletal and connective tissue disorders
Musculoskeletal pain | 47 | 0
Respiratory, thoracic, and mediastinal disorders
Dyspnea | 37 | 2.3
Cough | 25 | 0
Gastrointestinal disorders
Nausea | 36 | 0
Stomatitis | 26 | 0.8
Constipation | 23 | 0
Vomiting | 22 | 0
Diarrhea | 16 | 3.1
Abdominal Pain | 11 | 0.8
Vascular disorders
Hemorrhage | 19 | 0
Metabolism and nutrition disorders
Decreased appetite | 15 | 0
Nervous system disorders
Peripheral neuropathy | 13 | 0
Dizziness | 12 | 0.8
Headache | 10 | 0.8

Clinically relevant adverse reactions in < 10% of patients who received intravenous amivantamab included ocular toxicity, ILD/pneumonitis, and toxic epidermal necrolysis (TEN).

Table 19 summarizes the laboratory abnormalities in CHRYSALIS.

Table 19: Select Laboratory Abnormalities (≥ 20%) That Worsened from Baseline in Patients With Metastatic NSCLC with EGFR Exon 20 Insertion Mutations Whose Disease Has Progressed on or After Platinum-based Chemotherapy and Who Received Intravenous Amivantamab in CHRYSALIS
Laboratory Abnormality | Intravenous Amivantamab [The denominator used to calculate the rate was 126 based on the number of patients with a baseline value and at least one post-treatment value.] (N=129)
Laboratory Abnormality | All Grades (%) | Grades 3 or 4 (%)
Chemistry
Decreased albumin | 79 | 8
Increased glucose | 56 | 4
Increased alkaline phosphatase | 53 | 4.8
Increased creatinine | 46 | 0
Increased alanine aminotransferase | 38 | 1.6
Decreased phosphate | 33 | 8
Increased aspartate aminotransferase | 33 | 0
Decreased magnesium | 27 | 0
Increased gamma-glutamyl transferase | 27 | 4
Decreased sodium | 27 | 4
Decreased potassium | 26 | 6
Hematology
Decreased lymphocytes | 36 | 8

8 USE IN SPECIFIC POPULATIONS

8.1 Pregnancy

Risk Summary

Based on the mechanism of action [see Clinical Pharmacology (12.1)] and findings in animal models, RYBREVANT FASPRO can cause fetal harm when administered to a pregnant woman. There are no available data on the use of RYBREVANT FASPRO in pregnant women or animal data to assess the risk of RYBREVANT FASPRO in pregnancy. Disruption or depletion of EGFR in animal models resulted in impairment of embryo-fetal development including effects on placental, lung, cardiac, skin, and neural development. The absence of EGFR or MET signaling has resulted in embryo lethality, malformations, and post-natal death in animals (see Data). Advise pregnant women and females of reproductive potential of the potential risk to a fetus.

In the U.S. general population, the estimated background risk of major birth defects and miscarriage in clinically recognized pregnancies is 2% to 4% and 15% to 20%, respectively.

Data

Animal Data

RYBREVANT FASPRO for subcutaneous injection contains amivantamab and hyaluronidase [see Description (11)].

Amivantamab: No animal studies have been conducted to evaluate the effects of amivantamab on reproduction and fetal development; however, based on its mechanism of action, RYBREVANT FASPRO can cause fetal harm or developmental anomalies. In mice, EGFR is critically important in reproductive and developmental processes including blastocyst implantation, placental development, and embryo-fetal/postnatal survival and development. Reduction or elimination of embryo-fetal or maternal EGFR signaling can prevent implantation, can cause embryo-fetal loss during various stages of gestation (through effects on placental development) and can cause developmental anomalies and early death in surviving fetuses. Adverse developmental outcomes were observed in multiple organs in embryos/neonates of mice with disrupted EGFR signaling. Similarly, knock out of MET or its ligand HGF was embryonic lethal due to severe defects in placental development, and fetuses displayed defects in muscle development in multiple organs. Human IgG1 is known to cross the placenta; therefore, amivantamab has the potential to be transmitted from the mother to the developing fetus.

Hyaluronidase: In an embryo-fetal study, mice were dosed daily by subcutaneous injection during the period of organogenesis with hyaluronidase (recombinant human) at dose levels up to 2,200,000 U/kg, which is > 3600 times higher than the human dose. The study found no evidence of teratogenicity. Reduced fetal weight and increased numbers of fetal resorptions were observed, with no effects found at a daily dose of 360,000 U/kg, which is > 600 times higher than the human dose. In a peri-and post-natal reproduction study, mice have been dosed daily by subcutaneous injection, with hyaluronidase (recombinant human) from implantation through lactation and weaning at dose levels up to 1,100,000 U/kg, which is > 1800 times higher than the human dose. The study found no adverse effects on sexual maturation, learning and memory or fertility of the offspring.

8.2 Lactation

Risk Summary

There are no data on the presence of amivantamab or hyaluronidase in human milk or its effects on the breastfed child, or on milk production. Maternal IgG is known to be present in human milk. The effects of local gastrointestinal exposure and limited systemic exposure in the breastfed child to RYBREVANT FASPRO are unknown. Because of the potential for serious adverse reactions from RYBREVANT FASPRO in breastfed children, advise women not to breastfeed during treatment with RYBREVANT FASPRO and for 3 months after the last dose.

8.3 Females and Males of Reproductive Potential

RYBREVANT FASPRO can cause fetal harm when administered to a pregnant woman [see Use in Specific Populations (8.1)].

Pregnancy Testing

Verify pregnancy status of females of reproductive potential prior to initiating RYBREVANT FASPRO [see Warnings and Precautions (5.6) and Use in Specific Populations (8.1)].

Contraception

Females

Advise females of reproductive potential to use effective contraception during treatment and for 3 months after the last dose of RYBREVANT FASPRO.

8.4 Pediatric Use

The safety and efficacy of RYBREVANT FASPRO have not been established in pediatric patients.

8.5 Geriatric Use

Of the 206 patients with locally advanced or metastatic NSCLC treated with RYBREVANT FASPRO in combination with lazertinib (every 2-week dosing) in the PALOMA-3 study, 35% were ≥ 65 years of age, and 9% were ≥ 75 years of age.

The safety of RYBREVANT FASPRO in combination with other antineoplastic drugs or as a single agent for its approved indications [see Indications and Usage (1.1, 1.2, 1.3, 1.4)] has been established in adequate and well-controlled studies of intravenous amivantamab in combination with other antineoplastic drugs and as a single agent.

- Of the 421 patients with locally advanced or metastatic NSCLC treated with intravenous amivantamab in combination with lazertinib in the MARIPOSA study, 45% were ≥ 65 years of age and 12% were ≥ 75 years of age.
- Of the 130 patients with locally advanced or metastatic NSCLC treated with intravenous amivantamab in combination with carboplatin and pemetrexed in the MARIPOSA-2 study, 40% were ≥ 65 years of age and 10% were ≥ 75 years of age.
- Of the 151 patients with locally advanced or metastatic NSCLC treated with intravenous amivantamab in combination with carboplatin and pemetrexed in the PAPILLON study, 37% were ≥ 65 years of age and 8% were ≥ 75 years of age.
- Of the 302 patients with locally advanced or metastatic NSCLC treated with intravenous amivantamab as a single agent in the CHRYSALIS study, 39% were ≥ 65 years of age and 11% were ≥ 75 years of age.

No clinically important differences in safety or efficacy were observed between patients who were ≥ 65 years of age and younger patients.

11 DESCRIPTION

RYBREVANT FASPRO is a fixed-combination drug product containing amivantamab and hyaluronidase (human recombinant).

- Amivantamab is a low-fucose human immunoglobulin G1-based bispecific antibody directed against the EGF and MET receptors, produced by mammalian cell line (Chinese Hamster Ovary [CHO]) using recombinant DNA technology that has a molecular weight of approximately 148 kDa.
- Hyaluronidase (human recombinant) is an endoglycosidase used to increase the dispersion and absorption of co-administered drugs when administered subcutaneously. It is a glycosylated single-chain protein produced by CHO cells containing a DNA plasmid encoding for a soluble fragment of human hyaluronidase (PH20). Hyaluronidase (human recombinant) has a molecular weight of approximately 61 kDa.

RYBREVANT FASPRO™ (amivantamab and hyaluronidase-lpuj) injection for subcutaneous use is a sterile, preservative free, clear to opalescent and colorless to pale yellow solution supplied in a single-dose vial with a pH of 5.7.

Each RYBREVANT FASPRO 10 mL single-dose vial contains 1,600 mg of amivantamab and 20,000 units of hyaluronidase (human recombinant), edetate disodium (0.18 mg), glacial acetic acid (1.9 mg), methionine (10 mg), polysorbate 80 (6 mg), sodium acetate (22.1 mg), sucrose (710 mg), and Water for Injection, USP.

Each RYBREVANT FASPRO 14 mL single-dose vial contains 2,240 mg of amivantamab and 28,000 units of hyaluronidase (human recombinant), edetate disodium (0.25 mg), glacial acetic acid (2.6 mg), methionine (14 mg), polysorbate 80 (8.4 mg), sodium acetate (30.9 mg), sucrose (994 mg), and Water for Injection, USP.

Each RYBREVANT FASPRO 15 mL single-dose vial contains 2,400 mg of amivantamab and 30,000 units of hyaluronidase (human recombinant), edetate disodium (0.27 mg), glacial acetic acid (2.8 mg), methionine (15 mg), polysorbate 80 (9 mg), sodium acetate (33.1 mg), sucrose (1,065 mg), and Water for Injection, USP.

Each RYBREVANT FASPRO 22 mL single-dose vial contains 3,520 mg of amivantamab and 44,000 units of hyaluronidase (human recombinant), edetate disodium (0.4 mg), glacial acetic acid (4.1 mg), methionine (22 mg), polysorbate 80 (13.2 mg), sodium acetate (48.6 mg), sucrose (1,562 mg), and Water for Injection, USP.

12 CLINICAL PHARMACOLOGY

12.1 Mechanism of Action

Amivantamab is a bispecific antibody that binds to the extracellular domains of EGFR and MET.

In in vitro and in vivo studies, amivantamab was able to disrupt EGFR and MET signaling functions through blocking ligand binding and, in exon 19 deletions, exon 21 L858R substitutions, and exon 20 insertion mutation models, degradation of EGFR and MET. The presence of EGFR and MET on the surface of tumor cells also allows for targeting of these cells for destruction by immune effector cells, such as natural killer cells and macrophages, through antibody-dependent cellular cytotoxicity (ADCC) and trogocytosis mechanisms, respectively.

Hyaluronan is a polysaccharide found in the extracellular matrix of the subcutaneous tissue. It is depolymerized by the naturally occurring enzyme hyaluronidase. Unlike the stable structural components of the interstitial matrix, hyaluronan has a half-life of approximately 0.5 days.

Hyaluronidase increases permeability of the subcutaneous tissue by depolymerizing hyaluronan. In the doses administered, hyaluronidase in RYBREVANT FASPRO acts transiently and locally. The effects of hyaluronidase are reversible and permeability of the subcutaneous tissue is restored within 24 to 48 hours.

12.2 Pharmacodynamics

The exposure-response relationship and time-course of pharmacodynamic response of amivantamab have not been fully characterized in patients with NSCLC with EGFR mutations.

12.3 Pharmacokinetics

Amivantamab exposure and accumulation following the approved recommended dosages are provided in Table 20. Amivantamab exposure increases dose-proportionally across the recommended dosing regimens. Amivantamab maximum trough concentration is typically observed at the end of the weekly dosing (Cycle 2 Day 1). Amivantamab steady-state concentration is reached by approximately Week 13.

Table 20: Amivantamab Exposure and Accumulation
Dose | Frequency | Geometric Mean Ctrough,max (%CV) | Geometric Mean Ctrough,steady-state (%CV) | AUC1week Accumulation
1,600 mg amivantamab / 20,000 units hyaluronidase to 2,240 mg amivantamab / 28,000 units hyaluronidase | every 2-week | 335 µg/mL (33%) | 206 µg/mL (39%) | Increase 3.5-fold
2,400 mg amivantamab / 30,000 units hyaluronidase to 3,360 mg amivantamab / 42,000 units hyaluronidase | every 3-week | 464 µg/mL (24%) | 218 µg/mL (42%) | Increase 4.5-fold
3,520 mg amivantamab / 44,000 units hyaluronidase to 4,640 mg amivantamab / 58,000 units hyaluronidase | every 4-week | 350 µg/mL (31%) | 129 µg/mL (52%) | Increase 4.8-fold

Adult patients with NSCLC were randomized (1:1) to RYBREVANT FASPRO or intravenous amivantamab in combination with lazertinib in PALOMA-3, an open-label, randomized trial. The primary outcome measure was amivantamab steady-state Ctrough (Cycle 4 Day 1) and Cycle 2 AUCDay 1–15 of RYBREVANT FASPRO as compared to intravenous amivantamab. Additional descriptive efficacy outcome measures were overall response rate (ORR), progression-free survival (PFS), and overall survival (OS). Amivantamab exposure following administration of RYBREVANT FASPRO and intravenous amivantamab were comparable.

- At the recommended every 2-week dosage, the observed geometric mean ratios (GMRs) (90% CI) for Cycle 2 AUCDay 1–15 was 1.03 (0.98, 1.09) and for steady-state Ctrough (Cycle 4 Day 1) was 1.43 (1.27, 1.61).
- At the recommended every 3-week dosage, the simulated GMRs (90% CI) for average concentration of Cycle 2 Day 1 to Day 21 was 1.20 (1.15, 1.26) and steady-state Ctrough was 1.32 (1.23, 1.42).
- At the recommended every 4-week dosage, the simulated GMRs (90% CI) for average concentration of Cycle 2 Day 1 to Day 28 was 1.20 (1.15, 1.26) and steady-state Ctrough was 1.01 (0.93, 1.09).

Absorption

Amivantamab bioavailability is 67% (15%) with a median time to reach maximum concentration of 3 days following administration of RYBREVANT FASPRO.

Distribution

Amivantamab apparent volume of distribution is 5.7 L (24%).

Elimination

Amivantamab is cleared by parallel linear and nonlinear saturable target mediated clearances after subcutaneous administration. Amivantamab estimated terminal half-life is 19 days (34%) with an associated linear apparent clearance of 0.22 L/day (26%).

Specific Populations

No clinically significant differences in the pharmacokinetics of amivantamab were observed based on age (range: 28–85 years), baseline albumin level (range: 26–51 g/L), sex, race, ethnicity, mild and moderate renal impairment (creatinine clearance [CLCr] 29 to < 90 mL/min estimated by Cockcroft Gault equation), mild hepatic impairment [(total bilirubin ≤ ULN and AST > ULN) or (ULN < total bilirubin ≤ 1.5 times ULN)], Eastern Cooperative Oncology Group (ECOG) performance status, history of brain metastases, and EGFR primary mutation type. The effect of severe renal (CLCr 15 to 29 mL/min) impairment or moderate (total bilirubin 1.5 to 3 times ULN) to severe (total bilirubin > 3 times ULN) hepatic impairment on amivantamab pharmacokinetics is unknown.

Increases in body weight increased the volume of distribution and clearance of amivantamab. With the recommended dosages, exposures of amivantamab were comparable between patients who weighed < 80 kg and received 1,600 mg amivantamab and 20,000 units hyaluronidase (every 2-week dosing)/2,400 mg amivantamab and 30,000 units hyaluronidase (every 3-week dosing)/3,520 mg amivantamab and 44,000 units hyaluronidase (every 4-week dosing) and patients who weighed ≥ 80 kg and received 2,240 mg amivantamab and 28,000 units hyaluronidase (every 2-week dosing)/3,360 mg amivantamab and 42,000 units hyaluronidase (every 3-week dosing)/4,640 mg amivantamab and 58,000 units hyaluronidase (every 4-week dosing).

12.6 Immunogenicity

The observed incidence of anti-drug antibodies is highly dependent on the sensitivity and specificity of the assay. Differences in assay methods preclude meaningful comparisons of the incidence of anti-drug antibodies (ADA) in the studies described below with the incidence of anti-drug antibodies in other studies, including those of RYBREVANT FASPRO or other amivantamab products or other hyaluronidase products.

During the treatment period of up to 30 months across PALOMA, PALOMA-2, and PALOMA-3, 3/729 of patients (0.4%) who received RYBREVANT FASPRO as a single agent or in combination with lazertinib developed treatment emergent anti-amivantamab antibodies. Because of the low occurrence of anti-amivantamab antibodies, the effect of these antibodies on the pharmacokinetics, safety, and/or effectiveness of amivantamab products is unknown.

During the treatment period of up to 30 months across PALOMA, PALOMA-2 and PALOMA-3, 66/741 patients (9%) who received RYBREVANT FASPRO as a single agent or in combination with lazertinib developed treatment emergent anti-hyaluronidase (recombinant human, rHuPH20) antibodies and 2/66 patients (3%) tested positive for neutralizing antibodies. There was no identified clinically significant effect of anti-hyaluronidase antibodies on pharmacokinetics, safety, or effectiveness of RYBREVANT FASPRO.

13 NONCLINICAL TOXICOLOGY

13.1 Carcinogenesis, Mutagenesis, Impairment of Fertility

No studies have been performed to assess the potential of amivantamab for carcinogenicity or genotoxicity. Fertility studies have not been performed to evaluate the potential effects of amivantamab. In 6-week and 3-month repeat-dose toxicology studies in monkeys, there were no notable effects in the male and female reproductive organs.

Hyaluronidases are found in most tissues of the body. Long-term animal studies have not been performed to assess the carcinogenic or mutagenic potential of hyaluronidase. In addition, when hyaluronidase (recombinant human) was administered to cynomolgus monkeys for 39 weeks at dose levels up to 220,000 U/kg, which is >300 times higher than the human dose, no evidence of toxicity to the male or female reproductive system was found through periodic monitoring of in-life parameters, e.g., semen analyses, hormone levels, menstrual cycles, and also from gross pathology, histopathology and organ weight data.

14 CLINICAL STUDIES

The effectiveness of RYBREVANT FASPRO has been established based on adequate and well controlled studies of intravenous amivantamab:

- in combination with lazertinib for the first-line treatment of adult patients with locally advanced or metastatic non‑small cell lung cancer (NSCLC) with epidermal growth factor receptor (EGFR) exon 19 deletions or exon 21 L858R substitution mutations, as detected by an FDA-approved test [see Indications and Usage (1.1)]
- in combination with carboplatin and pemetrexed for the treatment of adult patients with locally advanced or metastatic NSCLC with EGFR exon 19 deletions or exon 21 L858R substitution mutations, whose disease has progressed on or after treatment with an EGFR tyrosine kinase inhibitor [see Indications and Usage (1.2)]
- in combination with carboplatin and pemetrexed for the first-line treatment of adult patients with locally advanced or metastatic NSCLC with EGFR exon 20 insertion mutations, as detected by an FDA-approved test [see Indications and Usage (1.3)]
- as a single agent for the treatment of adult patients with locally advanced or metastatic NSCLC with EGFR exon 20 insertion mutations, as detected by an FDA‑approved test whose disease has progressed on or after platinum‑based chemotherapy [see Indications and Usage (1.4)].

14.1 First-Line Treatment of NSCLC with EGFR Exon 19 Deletions or Exon 21 L858R Substitution Mutations – Intravenous Amivantamab in Combination with Lazertinib

MARIPOSA

The efficacy of intravenous amivantamab, in combination with lazertinib, was evaluated in MARIPOSA (NCT04487080), a randomized, active-controlled, multicenter trial. Eligible patients were required to have untreated locally advanced or metastatic NSCLC with either exon 19 deletions or exon 21 L858R substitution EGFR mutations identified by local testing, not amenable to curative therapy. Patients with asymptomatic or previously treated and stable intracranial metastases were eligible to enroll.

Patients were randomized (2:2:1) to receive intravenous amivantamab in combination with lazertinib (N=429), osimertinib monotherapy (N=429), or lazertinib monotherapy (an unapproved regimen for NSCLC) until disease progression or unacceptable toxicity. The evaluation of efficacy for the treatment of untreated metastatic NSCLC relied upon comparison between:

- Amivantamab administered intravenously at 1,050 mg (for patients < 80 kg) or 1,400 mg (for patients ≥ 80 kg) once weekly for 4 weeks, then every 2 weeks thereafter starting at week 5 in combination with lazertinib administered at 240 mg orally once daily.
- Osimertinib administered at a dose of 80 mg orally once daily.

Randomization was stratified by EGFR mutation type (exon 19 deletion or exon 21 L858R substitution mutation), Asian race (yes or no), and history of brain metastasis (yes or no). Tumor assessments were performed every 8 weeks for 30 months, and then every 12 weeks until disease progression.

The major efficacy outcome measure was progression-free survival (PFS) as assessed by blinded independent central review (BICR). Additional efficacy outcome measures included overall survival (OS), overall response rate (ORR), and duration of response (DOR).

A total of 858 patients were randomized between the two study arms, 429 to the intravenous amivantamab in combination with lazertinib arm and 429 to the osimertinib arm. The median age was 63 (range: 25–88) years; 61% were female; 58% were Asian, 38% were White, 1.6% were American Indian or Alaska Native, 0.8% were Black or African American, 0.2% were Native Hawaiian or other Pacific Islander, 0.6% were unknown race or multiple races; and 12% were Hispanic or Latino. Eastern Cooperative Oncology Group (ECOG) performance status was 0 (34%) or 1 (66%); 69% never smoked; 41% had prior brain metastases; and 89% had Stage IV cancer at initial diagnosis. Sixty percent of patients had tumors harboring exon 19 deletions and the remaining 40% had exon 21 L858R substitution mutations.

Among the 858 patients with EGFR exon 19 deletion or L858R substitution mutations that were randomized between the intravenous amivantamab plus lazertinib arm versus the osimertinib arm, available tissue samples from 544 (63%) patients had evaluable results when tested retrospectively using the cobas EGFR Mutation Test v2. Of the 544 patients with evaluable results, 527 (97%) patients were positive for EGFR exon 19 deletion or L858R substitution mutations, while 17 (3%) patients were negative. Available plasma samples from patients were retrospectively tested using an FDA-approved test to confirm the biomarker status.

The trial demonstrated a statistically significant improvement in PFS by BICR assessment and OS for intravenous amivantamab in combination with lazertinib compared to osimertinib (see Table 21 and Figures 1 and 2).

Efficacy results for intravenous amivantamab in combination with lazertinib are provided in Table 21.

Table 21: Efficacy Results in MARIPOSA by BICR Assessment
 | Intravenous amivantamab in combination with lazertinib (N=429) | Osimertinib (N=429)
Progression-free survival (PFS)
Number of events (%) | 192 (45) | 252 (59)
Median, months (95% CI) | 23.7 (19.1, 27.7) | 16.6 (14.8, 18.5)
HR [Stratified by mutation type (Exon 19del or Exon 21 L858R), prior brain metastases (yes or no), and Asian race (yes or no).] , [Stratified Cox proportional hazards regression.] (95% CI); p-value, [Stratified log-rank test.] | 0.70 (0.58, 0.85); p=0.0002
Overall survival (OS)
Number of events (%) | 173 (40) | 217 (51)
Median, months (95% CI) | NR (42.9, NE) | 36.7 (33.4, 41.0)
HR, (95% CI); p-value, | 0.75 (0.61, 0.92); p=0.0048
Overall response rate (ORR) [Confirmed responses based on the ITT population.]
ORR, % (95% CI) | 78 (74, 82) | 73 (69, 78)
Complete response, % | 5.4 | 3.5
Partial response, % | 73 | 70
Duration of response (DOR) [In confirmed responders.]
Median (95% CI), months | 25.8 (20.1, NE) | 16.7 (14.8, 18.5)
Patients with DOR ≥ 6 months [Based on observed rates.] , % | 86 | 85
Patients with DOR ≥ 12 months, % | 68 | 57
CI = confidence interval; NR = not reached; NE = not estimable

Figure 1: Kaplan-Meier Curves of PFS by BICR Assessment in Patients with Previously Untreated NSCLC

Figure 2: Kaplan-Meier Curves of OS in Patients with Previously Untreated NSCLC

Out of all randomized patients (n=858), 367 (43%) had baseline intracranial lesions assessed by BICR using modified RECIST. Results of pre-specified analyses of intracranial ORR and DOR by BICR in the subset of patients with intracranial lesions at baseline for the intravenous amivantamab in combination with lazertinib arm and the osimertinib arm are summarized in Table 22.

Table 22: Exploratory Analysis of Intracranial ORR and DOR by BICR Assessment in Subjects with Intracranial Lesions at Baseline
 | Intravenous amivantamab in combination with lazertinib (N=180) | Osimertinib (N=187)
Intracranial tumor response assessment
Intracranial ORR [Confirmed responses] , % (95% CI) | 68 (60, 75) | 69 (62, 76)
Complete response % | 55 | 52
Intracranial DOR [In confirmed responders]
Number of responders | 122 | 129
Patients with DOR ≥ 12 months [Based on observed rates] , % | 66 | 59
Patients with DOR ≥ 18 months, % | 35 | 23
CI = confidence interval

14.2 Previously Treated NSCLC with EGFR Exon 19 Deletions or Exon 21 L858R Substitution Mutations – Intravenous Amivantamab in Combination with Carboplatin and Pemetrexed

MARIPOSA-2

The efficacy of intravenous amivantamab in combination with carboplatin and pemetrexed was evaluated in MARIPOSA-2 (NCT04988295), a randomized, open-label, multicenter trial. Eligible patients were required to have locally advanced or metastatic NSCLC with EGFR exon 19 deletions or exon 21 L858R substitution mutations and progressive disease on or after receiving osimertinib. Patients with asymptomatic or previously treated and stable intracranial metastases were eligible to enroll. Patients were randomized (1:2:2) to receive intravenous amivantamab in combination with carboplatin and pemetrexed (intravenous amivantamab-CP, N=131), carboplatin and pemetrexed (CP, N=263), or intravenous amivantamab as part of another combination regimen. The evaluation of efficacy for metastatic NSCLC relied upon comparison between:

- Intravenous amivantamab in combination with carboplatin and pemetrexed.
  Amivantamab was administered intravenously at 1,400 mg (for patients < 80 kg) or 1,750 mg (for patients ≥ 80 kg) once weekly through 4 weeks, then every 3 weeks with a dose of 1,750 mg (for patients < 80 kg) or 2,100 mg (for patients ≥ 80 kg) starting at Week 7 until disease progression or unacceptable toxicity.
- Platinum-based chemotherapy with carboplatin and pemetrexed.

For both arms, carboplatin was administered intravenously at area under the concentration-time curve 5 mg/mL per minute (AUC 5) once every 3 weeks, for up to 12 weeks and pemetrexed was administered intravenously at 500 mg/m^2 once every 3 weeks until disease progression or unacceptable toxicity.

Randomization was stratified by osimertinib line of therapy (first-line or second-line), prior brain metastases (yes or no), and Asian race (yes or no). Tumor assessments were performed every 6 weeks for the first 12 months and every 12 weeks thereafter.

The major efficacy outcome measure was progression-free survival (PFS) as assessed by blinded independent central review (BICR). Overall survival (OS) and overall response rate (ORR) as assessed by BICR were key secondary outcome measures.

A total of 394 patients were randomized between the two arms, 131 to the intravenous amivantamab-CP arm and 263 to the CP arm. The median age was 62 (range: 31 to 85) years, with 38% of patients ≥ 65 years of age; 60% were female; and 48% were Asian and 46% were White, 1% were American Indian or Alaska Native, 1% were Black or African American, 0.5% were multiple races and 2.8% were race not reported or race unknown; 8% were Hispanic or Latino.

Baseline Eastern Cooperative Oncology Group (ECOG) performance status was 0 (40%) or 1 (60%); 65% never smoked; 45% had history of brain metastasis, and 99.7% had Stage IV cancer at study enrollment.

The trial demonstrated a statistically significant improvement in PFS by BICR for intravenous amivantamab in combination with carboplatin and pemetrexed compared to carboplatin and pemetrexed.

Efficacy results are summarized in Table 23.

Table 23: Efficacy Results in MARIPOSA-2
 | Intravenous amivantamab with carboplatin and pemetrexed (N=131) | carboplatin and pemetrexed (N=263)
Progression-free survival (PFS) [Blinded Independent Central Review by RECIST v1.1.]
Number of events | 74 (56%) | 171 (65%)
Median, months (95% CI) | 6.3 (5.6, 8.4) | 4.2 (4.0, 4.4)
HR (95% CI) [Stratified by osimertinib line of therapy (first-line or second-line), prior brain metastases (yes or no), and Asian race (yes or no).] , [Stratified Cox proportional hazards regression.] ; p-value, [Stratified log-rank test.] | 0.48 (0.36, 0.64); p<0.0001
Overall response rate, [Confirmed responses.]
ORR, % (95% CI) | 53% (44, 62) | 29% (23, 35)
p-value, [Stratified logistic regression analysis.] | p<0.0001
Complete response | 0.8% | 0%
Partial response | 52% | 29%
Duration of response, (DOR)
Median (95% CI), months | 6.9 (5.5, NE) | 5.6 (4.2, 9.6)
CI = confidence interval; NE = not estimatable

Figure 3: Kaplan-Meier Curve of PFS in Previously Treated NSCLC Patients by BICR Assessment - MARIPOSA-2

At the prespecified second interim analysis of OS, with 85% of the deaths needed for the final analysis, there was no statistically significant difference in OS. The median OS was 17.7 months (95% CI: 16.0, 22.4) in the ACP arm and 15.3 months (95% CI: 13.7, 16.8) in the CP arm, with a hazard ratio of 0.73 (95% CI: 0.54, 0.99).

Patients with asymptomatic or previously treated and stable intracranial metastases were eligible to be randomized in MARIPOSA-2. Baseline disease assessment, including brain magnetic resonance imaging (MRI) was performed at treatment initiation. All patients underwent serial brain MRI during the trial.

Pre-specified secondary analyses of intracranial ORR by BICR in the subset of 91 (23%) patients with baseline intracranial disease were performed. Data were only available for intracranial complete responses and not available for intracranial partial responses. Intracranial ORR was 20% (95% CI: 8, 39) in the 30 patients with baseline intracranial disease in the ACP arm and 7% (95% CI: 1.8, 16) in the 61 patients with baseline intracranial disease in the CP arm.

14.3 First-Line Treatment of NSCLC with EGFR Exon 20 Insertion Mutations – Intravenous Amivantamab in Combination with Carboplatin and Pemetrexed

PAPILLON

The efficacy of intravenous amivantamab was evaluated in PAPILLON (NCT04538664), in a randomized, open-label, multicenter study. Eligible patients were required to have previously untreated locally advanced or metastatic NSCLC with EGFR Exon 20 insertion mutations measurable disease per RECIST v1.1, Eastern Cooperative Oncology Group (ECOG) performance status (PS) ≤ 1, and adequate organ and bone marrow function. Patients with brain metastases at screening were eligible for participation once they were definitively treated, clinically stable, asymptomatic, and off corticosteroid treatment for at least 2 weeks prior to randomization. Patients with a medical history of interstitial lung disease or active ILD were excluded from the clinical study.

A total of 308 patients were randomized 1:1 to receive intravenous amivantamab in combination with carboplatin and pemetrexed (n=153) or carboplatin and pemetrexed (n=155). Patients received amivantamab intravenously at 1,400 mg (for patients < 80 kg) or 1,750 mg (for patients ≥ 80 kg) once weekly through 4 weeks, then every 3 weeks with a dose of 1,750 mg (for patients < 80 kg) or 2,100 mg (for patients ≥ 80 kg) starting at Week 7 until disease progression or unacceptable toxicity. Carboplatin was administered intravenously at area under the concentration-time curve 5 mg/mL per minute (AUC 5) once every 3 weeks, for up to 12 weeks. Pemetrexed was administered intravenously at 500 mg/m^2 on once every 3 weeks until disease progression or unacceptable toxicity. Patients were stratified by Eastern Cooperative Oncology Group (ECOG) performance status (0 or 1) and prior brain metastases (yes or no).

The primary efficacy outcome measure was progression-free survival (PFS) as assessed by blinded independent central review (BICR). Additional efficacy outcome measures included overall response rate (ORR), duration of response (DOR) and overall survival (OS). Cross-over to single agent intravenous amivantamab was permitted for patients who had confirmed disease progression on carboplatin and pemetrexed.

The median age was 62 (range: 27 to 92) years, with 40% of the patients ≥ 65 years of age; 58% were female; 61% were Asian and 36% were White, 0.7% were Black or African American and race was not reported in 2.3% of patients; 93% were not Hispanic or Latino. Baseline ECOG performance status was 0 (35%) or 1 (65%); 58% were never smokers; 23% had history of brain metastasis and 84% had Stage IV cancer at initial diagnosis.

PAPILLON demonstrated a statistically significant improvement in progression free survival for patients randomized to intravenous amivantamab in combination with carboplatin and pemetrexed compared with carboplatin and pemetrexed.

Efficacy results are summarized in Table 24 and Figure 4.

Table 24: Efficacy Results in PAPILLON
 | Intravenous amivantamab with carboplatin and pemetrexed (N=153) | carboplatin and pemetrexed (N=155)
Progression-Free Survival (PFS)
Number of events (%) | 84 (55) | 132 (85)
Median, months (95% CI) | 11.4 (9.8, 13.7) | 6.7 (5.6, 7.3)
HR (95% CI) | 0.40 (0.30, 0.53)
p-value | p<0.0001
Overall Response Rate (ORR) [Confirmed responses.]
ORR, % (95% CI) | 67 (59, 75) | 36 (29, 44)
Complete response, % | 4 | 1
Partial response, % | 63 | 36
Duration of response (DOR) [In confirmed responders.]
Median (95% CI), months | 10.1 (8.5, 13.9) | 5.6 (4.4, 6.9)
CI = confidence interval

Figure 4: Kaplan-Meier Curve of PFS in Previously Untreated NSCLC Patients by BICR Assessment – PAPILLON Study

While OS results were immature at the current analysis, with 44% of pre-specified deaths for the final analysis reported, no trend towards a detriment was observed. Seventy-five (48%) of the treated patients crossed over from the carboplatin and pemetrexed arm after confirmation of disease progression to receive intravenous amivantamab as a single agent.

14.4 Previously Treated NSCLC with EGFR Exon 20 Insertion Mutations – Intravenous Amivantamab as a Single Agent

CHRYSALIS

The efficacy of intravenous amivantamab was evaluated in patients with locally advanced or metastatic NSCLC with EGFR exon 20 insertion mutations in a multicenter, open-label, multi-cohort clinical trial (CHRYSALIS, NCT02609776). The study included patients with locally advanced or metastatic NSCLC with EGFR exon 20 insertion mutations whose disease had progressed on or after platinum-based chemotherapy. Patients with untreated brain metastases and patients with a history of ILD requiring treatment with prolonged steroids or other immunosuppressive agents within the last 2 years were not eligible for the study.

In the efficacy population, EGFR exon 20 insertion mutation status was determined by prospective local testing using tissue (94%) and/or plasma (6%) samples. Of the 81 patients with EGFR exon 20 insertion mutations identified by local testing, plasma samples from 78/81 (96%) patients were tested retrospectively using Guardant360® CDx, identifying 62/78 (79%) samples with an EGFR exon 20 insertion mutation; 16/78 (21%) samples did not have an EGFR exon 20 insertion mutation identified.

Patients received intravenous amivantamab at 1,050 mg (for patient baseline body weight < 80 kg) or 1,400 mg (for patient baseline body weight ≥ 80 kg) once weekly for 4 weeks, then every 2 weeks thereafter until disease progression or unacceptable toxicity. The major efficacy outcome measure was overall response rate (ORR) according to Response Evaluation Criteria in Solid Tumors (RECIST v1.1) as evaluated by Blinded Independent Central Review (BICR). An additional efficacy outcome measure was duration of response (DOR) by BICR.

The efficacy population included 81 patients with NSCLC with EGFR exon 20 insertion mutation with measurable disease who were previously treated with platinum-based chemotherapy. The median age was 62 (range: 42 to 84) years, 59% were female; 49% were Asian, 37% were White, 2.5% were Black; 74% had baseline body weight < 80 kg; 95% had adenocarcinoma; and 46% had received prior immunotherapy. The median number of prior therapies was 2 (range: 1 to 7). At baseline, 67% had Eastern Cooperative Oncology Group (ECOG) performance status of 1; 53% never smoked; all patients had metastatic disease; and 22% had previously treated brain metastases.

Efficacy results are summarized in Table 25.

Table 25: Efficacy Results for CHRYSALIS
 | Prior Platinum-based Chemotherapy Treated (N=81)
Overall Response Rate (95% CI) | 40% (29%, 51%)
Complete response (CR) | 3.7%
Partial response (PR) | 36%
Duration of Response (DOR)
Median (95% CI), months | 11.1 (6.9, NE)
Patients with DOR ≥ 6 months | 63%
Based on Kaplan-Meier estimates.
NE=Not Estimable, CI=confidence interval.

16 HOW SUPPLIED/STORAGE AND HANDLING

How Supplied

RYBREVANT FASPRO™ (amivantamab and hyaluronidase-lpuj) injection for subcutaneous use is a sterile, preservative free, clear to opalescent and colorless to pale yellow solution supplied as follows:

Strength | NDC
1,600 mg amivantamab and 20,000 units hyaluronidase per 10 mL (160 mg and 2,000 units per mL) | NDC 57894-510-01
2,240 mg amivantamab and 28,000 units hyaluronidase per 14 mL (160 mg and 2,000 units per mL) | NDC 57894-514-01
2,400 mg amivantamab and 30,000 units hyaluronidase per 15 mL (160 mg and 2,000 units per mL) | NDC 57894-515-01
3,520 mg amivantamab and 44,000 units hyaluronidase per 22 mL (160 mg and 2,000 units per mL) | NDC 57894-522-01

Storage and Handling

Store RYBREVANT FASPRO vials in a refrigerator at 2 °C to 8 °C (36 °F to 46 °F) in original carton to protect from light. Do not freeze. Do not shake.

17 PATIENT COUNSELING INFORMATION

Advise the patient to read the FDA-approved patient labeling (Patient Information).

Hypersensitivity and Administration-Related Reactions

Advise patients that RYBREVANT FASPRO can cause hypersensitivity and administration-related reactions, the majority of which may occur with the first injection. Advise patients to alert their healthcare provider immediately for any signs or symptoms of administration-related reactions during treatment with RYBREVANT FASPRO [see Warnings and Precautions (5.1)].

Interstitial Lung Disease/Pneumonitis

Advise patients that RYBREVANT FASPRO can cause interstitial lung disease (ILD)/pneumonitis. Advise patients to immediately contact their healthcare provider for new or worsening respiratory symptoms during treatment with RYBREVANT FASPRO [see Warnings and Precautions (5.2)].

Venous Thromboembolic Events with Concomitant Use with Lazertinib

Advise patients that when RYBREVANT FASPRO is used in combination with lazertinib, it can cause serious and life threatening venous thromboembolic events (VTE), including deep venous thrombosis and pulmonary embolism. Advise patients that prophylactic anticoagulants are recommended to be used for the first four months of treatment. Advise patients to immediately contact their healthcare provider for signs and symptoms of VTE during treatment with RYBREVANT FASPRO [see Warnings and Precautions (5.3)].

Dermatologic Adverse Reactions

Advise patients that RYBREVANT FASPRO can cause dermatologic adverse reactions. Advise patients that prophylactic oral antibiotics are recommended starting on Day 1 for the first 12 weeks of treatment and, after completion of oral antibiotic treatment, topical antibiotic lotion to the scalp for the next 9 months of treatment. Advise patients to use a non-comedogenic skin moisturizer (ceramide-based or other formulations that provide long-lasting skin hydration and exclude drying components) on the face and whole body (except scalp) and 4% chlorhexidine solution to wash hands and feet, while on treatment. Advise patients to limit direct sun exposure during and for 2 months after treatment, to wear protective clothing, and to use broad-spectrum UVA/UVB sunscreen to reduce the risk and severity of dermatologic adverse reactions [see Warnings and Precautions (5.4)].

Ocular Toxicity

Advise patients that RYBREVANT FASPRO can cause ocular toxicity. Advise patients to contact their ophthalmologist if they develop eye symptoms and advise discontinuation of contact lenses until symptoms are evaluated [see Warnings and Precautions (5.5)].

Paronychia/Nail toxicity

Advise patients that RYBREVANT FASPRO can cause paronychia. Advise patients to contact their healthcare provider for signs or symptoms of paronychia [see Adverse Reactions (6.1)].

Embryo-Fetal Toxicity

Advise females of reproductive potential of the potential risk to a fetus, to use effective contraception during treatment with RYBREVANT FASPRO and for 3 months after the last dose, and to inform their healthcare provider of a known or suspected pregnancy [see Warnings and Precautions (5.6) and Use in Specific Populations (8.1, 8.3)].

Lactation

Advise women not to breastfeed during treatment with RYBREVANT FASPRO and for 3 months after the last dose [see Use in Specific Populations (8.2)].

Manufactured by:

Janssen Biotech, Inc.
Horsham, PA 19044, USA
U.S. License Number 1864

Halozyme, Inc.
San Diego, CA 92130, USA
U.S. License Number 2187

For patent information: www.janssenpatents.com
© Johnson & Johnson and its affiliates 2025–2026

PATIENT INFORMATION
RYBREVANT (RYE-breh-vant) FASPRO™ (Fas-pro)
(amivantamab and hyaluronidase-lpuj)
injection, for subcutaneous use

What is RYBREVANT FASPRO?
RYBREVANT FASPRO is a prescription medicine used to treat adults with non-small cell lung cancer (NSCLC) that has spread to other parts of the body (metastatic) or cannot be removed by surgery, and has certain abnormal epidermal growth factor receptor (EGFR) gene(s):

- in combination with lazertinib as a first-line treatment for NSCLC
- in combination with carboplatin and pemetrexed for NSCLC in people whose disease has worsened on or after treatment with an EGFR tyrosine kinase inhibitor (TKI)
- in combination with carboplatin and pemetrexed as a first-line treatment for NSCLC
- alone for the treatment of NSCLC in people whose disease has worsened on or after platinum-based chemotherapy.

Your healthcare provider will perform a test to make sure that RYBREVANT FASPRO is right for you.
It is not known if RYBREVANT FASPRO is safe and effective in children.

Do not receive RYBREVANT FASPRO if you are allergic to hyaluronidase or any of the ingredients in RYBREVANT FASPRO. See the end of this leaflet for a complete list of ingredients in RYBREVANT FASPRO.

Before you receive RYBREVANT FASPRO, tell your healthcare provider about all of your medical conditions, including if you:

- have a history of lung or breathing problems, other than cancer.
- are pregnant or plan to become pregnant. RYBREVANT FASPRO can harm your unborn baby.
  Females who are able to become pregnant:
  - Your healthcare provider should do a pregnancy test before you start treatment with RYBREVANT FASPRO.
  - You should use effective birth control (contraception) during treatment and for 3 months after your last dose of RYBREVANT FASPRO.
  - Tell your healthcare provider right away if you become pregnant or think you might be pregnant during treatment with RYBREVANT FASPRO.
- are breastfeeding or plan to breastfeed. It is not known if RYBREVANT FASPRO passes into your breast milk. Do not breastfeed during treatment and for 3 months after your last dose of RYBREVANT FASPRO.

Tell your healthcare provider about all the medicines you take, including prescription and over-the-counter medicines, vitamins, and herbal supplements.

How will I receive RYBREVANT FASPRO?

- RYBREVANT FASPRO will be given to you by your healthcare provider as an injection under the skin (subcutaneous injection), in the stomach area (abdomen).
- RYBREVANT FASPRO is injected over about 5 minutes for each injection.
- Your healthcare provider will decide the time between doses as well as how many treatments you will receive.
- Your healthcare provider will give you medicines before each dose of RYBREVANT FASPRO to help reduce the risk and severity of allergic and injection-related reactions.
- Your healthcare provider may give you medicines in addition to RYBREVANT FASPRO to reduce the risk and severity of skin and nail reactions.
- RYBREVANT FASPRO may be given in combination with the medicines, carboplatin and pemetrexed. If you have any questions about these medicines, ask your healthcare provider.
- If your treatment with RYBREVANT FASPRO is given in combination with the medicine lazertinib, you should take your dose of lazertinib by mouth anytime before your injection with RYBREVANT FASPRO.
- If you miss any appointments, call your healthcare provider as soon as possible to reschedule your appointment.

What should I avoid while receiving RYBREVANT FASPRO?
RYBREVANT FASPRO can cause skin reactions. You should limit your time in the sun during and for 2 months after your treatment with RYBREVANT FASPRO. Wear protective clothing and use broad-spectrum sunscreen during treatment with RYBREVANT FASPRO.

What are the possible side effects of RYBREVANT FASPRO?
RYBREVANT FASPRO may cause serious side effects, including:

- allergic and injection-related reactions. Allergic and injection-related reactions are common and can be severe or serious. Tell your healthcare provider right away if you get any of the following symptoms during or after your injection of RYBREVANT FASPRO:

- shortness of breath
- fever
- chills
- flushing

- chest discomfort
- dizziness or lightheadedness
- vomiting

- lung problems. RYBREVANT FASPRO can cause lung problems that can lead to death. Symptoms may be similar to those symptoms from lung cancer. Tell your healthcare provider right away if you get any new or worsening lung symptoms, including:

- shortness of breath

- cough

- fever

- blood clot problems. RYBREVANT FASPRO, when given in combination with lazertinib, can cause blood clots in the veins of your legs (deep vein thrombosis) or lungs (pulmonary embolism) that can lead to death. Your healthcare provider may start you on medicine to prevent blood clots for the first 4 months of treatment. Tell your healthcare provider right away if you get any signs and symptoms of blood clots, including:
  - swelling, pain or tenderness in the leg
  - sudden unexplained chest pain
  - shortness of breath
- skin problems. RYBREVANT FASPRO can cause severe rash; including blisters, peeling, skin pain and sores, redness, raised acne-like bumps, itching, and dry skin. Your healthcare provider may start you on an antibiotic for the first 3 months of treatment followed by an antibiotic lotion for your scalp for the next 9 months. During treatment with RYBREVANT FASPRO, you should apply a non-comedogenic (does not clog pores) skin moisturizer (ceramide-based or other types of moisturizers that provide long-lasting skin hydration and does not include drying ingredients) on your face and whole body (except scalp) and wash your hands and feet every day with 4% chlorhexidine solution. Tell your healthcare provider right away if you get any skin reactions. Your healthcare provider may treat you with a medicine(s) or send you to see a skin specialist (dermatologist) if you get skin reactions during treatment with RYBREVANT FASPRO. See "What should I avoid while receiving RYBREVANT FASPRO?"
- eye problems. RYBREVANT FASPRO can cause eye problems. Tell your healthcare provider right away if you get symptoms of eye problems which may include:

- eye pain
- inflammation of eyelids
- dry eyes
- eye redness
- blurred vision

- changes in vision
- itchy eyes
- excessive tearing
- sensitivity to light

Your healthcare provider may send you to see an eye specialist (ophthalmologist) if you get new or worsening eye problems during treatment with RYBREVANT FASPRO. You should not use contact lenses until your eye symptoms are checked by a healthcare provider.

The most common side effects of RYBREVANT FASPRO in combination with lazertinib include:

- rash
- infected skin around the nail
- muscle and joint pain
- feeling very tired
- sores in the mouth
- swelling of hands, ankles, feet, face, or all of your body

- nausea
- diarrhea
- vomiting
- constipation
- decreased appetite
- headache
- changes in certain blood tests

The most common side effects observed with intravenous (IV) amivantamab, which may be experienced with RYBREVANT FASPRO are listed below.
The most common side effects of IV amivantamab in combination with lazertinib include:

- rash
- infected skin around the nail
- infusion-related reactions
- muscle and joint pain
- sores in the mouth
- swelling of hands, ankles, feet, face, or all of your body
- unusual feeling in the skin (such as tingling or a crawling feeling)
- feeling very tired

- diarrhea
- constipation
- COVID-19
- bleeding
- dry skin
- decreased appetite
- itching
- nausea
- changes in certain blood tests

The most common side effects of IV amivantamab in combination with carboplatin and pemetrexed include:

- rash
- infected skin around the nail
- infusion-related reactions
- feeling very tired
- nausea
- sores in the mouth
- constipation

- swelling of hands, ankles, feet, face, or all of your body
- decreased appetite
- muscle and joint pain
- vomiting
- COVID-19
- changes in certain blood tests

The most common side effects of IV amivantamab when given alone include:

- rash
- infusion-related reactions
- infected skin around the nail
- muscle and joint pain
- shortness of breath
- nausea
- swelling of hands, ankles, feet, face, or all of your body

- cough
- feeling very tired
- sores in the mouth
- constipation
- vomiting
- changes in certain blood tests

Your healthcare provider may temporarily stop, decrease your dose or completely stop your treatment with RYBREVANT FASPRO if you have serious side effects.
These are not all of the possible side effects of RYBREVANT FASPRO.
Call your doctor for medical advice about side effects. You may report side effects to FDA at 1-800-FDA-1088.

General information about safe and effective use of RYBREVANT FASPRO.
Medicines are sometimes prescribed for purposes other than those listed in a Patient Information leaflet. You can ask your healthcare provider or pharmacist for information about RYBREVANT FASPRO that is written for health professionals.

What are the ingredients of RYBREVANT FASPRO?
Active ingredient: amivantamab and hyaluronidase-lpuj
Inactive ingredients: edetate disodium, glacial acetic acid, methionine, polysorbate 80, sodium acetate, sucrose, and Water for Injection.

Manufactured by: Janssen Biotech, Inc., Horsham, PA 19044, USA. U.S. License Number 1864
Halozyme, Inc., San Diego, CA 92130, USA. U.S. License Number 2187
For patent information: www.janssenpatents.com
© Johnson & Johnson and its affiliates 2025–2026
For more information, call 1-800-526-7736 or go to www.RYBREVANT.com.

This Patient Information has been approved by the U.S. Food and Drug Administration.

Revised: 02/2026

PRINCIPAL DISPLAY PANEL - 10 mL Vial Carton

NDC 57894-510-01

Rybrevant Faspro™
(amivantamab and
hyaluronidase-lpuj)
Injection

1,600 mg and
20,000 units/10 mL

(160 mg and 2,000 units/mL)

For subcutaneous injection
by a healthcare provider only.

Administer each injection over
approximately 5 minutes.

Single-dose vial
Discard unused portion.

Rx only

One 10 mL Vial

Johnson
& Johnson

PRINCIPAL DISPLAY PANEL - 14 mL Vial Carton

NDC 57894-514-01

Rybrevant Faspro™
(amivantamab and
hyaluronidase-lpuj)
Injection

2,240 mg and
28,000 units/14 mL

(160 mg and 2,000 units/mL)

For subcutaneous injection
by a healthcare provider only.

Administer each injection over
approximately 5 minutes.

Single-dose vial
Discard unused portion.

Rx only

One 14 mL Vial

Johnson
& Johnson

PRINCIPAL DISPLAY PANEL - 15 mL Vial Carton

NDC 57894-515-01

Rybrevant Faspro™
(amivantamab and
hyaluronidase-lpuj)
Injection

2,400 mg and
30,000 units/15 mL

(160 mg and 2,000 units/mL)

For subcutaneous injection
by a healthcare provider only.

Administer each injection over
approximately 5 minutes.

Single-dose vial
Discard unused portion.

Rx only

One 15 mL Vial

Johnson
& Johnson

PRINCIPAL DISPLAY PANEL -22 mL Vial Carton

NDC 57894-522-01

Rybrevant Faspro™
(amivantamab and
hyaluronidase-lpuj)
Injection

3,520 mg and
44,000 units/22 mL

(160 mg and 2,000 units/mL)

For subcutaneous injection
by a healthcare provider only.

Administer each injection over
approximately 5 minutes.

Single-dose vial
Discard unused portion.

Rx only

One 22 mL Vial

Johnson
& Johnson